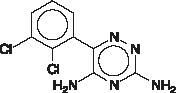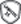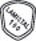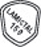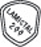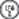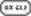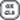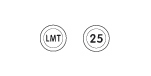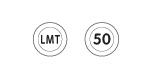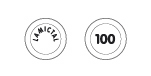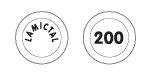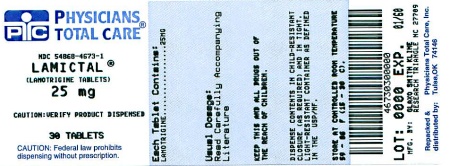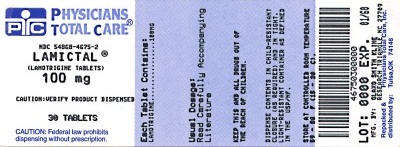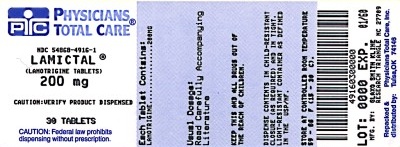 DRUG LABEL: LAMICTAL
NDC: 54868-4673 | Form: TABLET
Manufacturer: Physicians Total Care, Inc.
Category: prescription | Type: HUMAN PRESCRIPTION DRUG LABEL
Date: 20111221

ACTIVE INGREDIENTS: LAMOTRIGINE 25 mg/1 1
INACTIVE INGREDIENTS: LACTOSE; MAGNESIUM STEARATE; CELLULOSE, MICROCRYSTALLINE; POVIDONE; SODIUM STARCH GLYCOLATE TYPE A POTATO

HIGHLIGHTS OF PRESCRIBING INFORMATION

These highlights do not include all the information needed to use LAMICTAL safely and effectively. See full prescribing information for LAMICTAL.
LAMICTAL (lamotrigine) Tablets
LAMICTAL (lamotrigine) Chewable Dispersible Tablets
LAMICTAL ODT (lamotrigine) Orally Disintegrating Tablets
Initial U.S. Approval: 1994

RECENT MAJOR CHANGES

Warnings and Precautions, Multiorgan Hypersensitivity Reactions and Organ Failure (5.2) | August 2011

WARNING: SERIOUS SKIN RASHES

See full prescribing information for complete boxed warning.

Cases of life-threatening serious rashes, including Stevens-Johnson syndrome, toxic epidermal necrolysis, and/or rash-related death, have been caused by LAMICTAL. The rate of serious rash is greater in pediatric patients than in adults. Additional factors that may increase the risk of rash include (5.1):

- coadministration with valproate
- exceeding recommended initial dose of LAMICTAL
- exceeding recommended dose escalation of LAMICTAL

Benign rashes are also caused by LAMICTAL; however, it is not possible to predict which rashes will prove to be serious or life threatening. LAMICTAL should be discontinued at the first sign of rash, unless the rash is clearly not drug related. (5.1)

1 INDICATIONS AND USAGE

LAMICTAL is an antiepileptic drug (AED) indicated for:

Epilepsy—adjunctive therapy in patients ≥2 years of age: (1.1)

- partial seizures.
- primary generalized tonic-clonic seizures.
- generalized seizures of Lennox-Gastaut syndrome.

Epilepsy—monotherapy in patients ≥16 years of age: conversion to monotherapy in patients with partial seizures who are receiving treatment with carbamazepine, phenobarbital, phenytoin, primidone, or valproate as the single AED. (1.1)

Bipolar Disorder in patients ≥18 years of age: maintenance treatment of Bipolar I Disorder to delay the time to occurrence of mood episodes in patients treated for acute mood episodes with standard therapy. (1.2)

2 DOSAGE AND ADMINISTRATION

- Dosing is based on concomitant medications, indication, and patient age. (2.2, 2.4)
- To avoid an increased risk of rash, the recommended initial dose and subsequent dose escalations should not be exceeded. LAMICTAL Starter Kits and LAMICTAL ODT Patient Titration Kits are available for the first 5 weeks of treatment. (2.1, 16)
- Do not restart LAMICTAL in patients who discontinued due to rash unless the potential benefits clearly outweigh the risks. (2.1)
- Adjustments to maintenance doses will in most cases be required in patients starting or stopping estrogen-containing oral contraceptives. (2.1, 5.8)
- LAMICTAL should be discontinued over a period of at least 2 weeks (approximately 50% reduction per week). (2.1, 5.9)

Epilepsy

- Adjunctive therapy—See Table 1 for patients >12 years of age and Tables 2 and 3 for patients 2 to 12 years. (2.2)
- Conversion to monotherapy—See Table 4. (2.3)

Bipolar Disorder: See Tables 5 and 6. (2.4)

3 DOSAGE FORMS AND STRENGTHS

Tablets: 25 mg, 100 mg, 150 mg, and 200 mg scored. (3.1, 16)

Chewable Dispersible Tablets: 2 mg, 5 mg, and 25 mg. (3.2, 16)

Orally Disintegrating Tablets: 25 mg, 50 mg, 100 mg, and 200 mg. (3.3, 16)

4 CONTRAINDICATIONS

Hypersensitivity to the drug or its ingredients. (Boxed Warning, 4)

5 WARNINGS AND PRECAUTIONS

- Life-threatening serious rash and/or rash-related death may result. (Boxed Warning, 5.1)
- Fatal or life-threatening hypersensitivity reaction: Multiorgan hypersensitivity reactions, also known as Drug Reaction with Eosinophilia and Systemic Symptoms (DRESS), may be fatal or life threatening. Early signs may include rash, fever, and lymphadenopathy. These reactions may be associated with other organ involvement, such as hepatitis, hepatic failure, blood dyscrasias, or acute multiorgan failure. LAMICTAL should be discontinued if alternate etiology for this reaction is not found. (5.2)
- Blood dyscrasias (e.g., neutropenia, thrombocytopenia, pancytopenia): May occur, either with or without an associated hypersensitivity syndrome. (5.3)
- Suicidal behavior and ideation. (5.4)
- Clinical worsening, emergence of new symptoms, and suicidal ideation/behaviors may be associated with treatment of bipolar disorder. Patients should be closely monitored, particularly early in treatment or during dosage changes. (5.5)
- Aseptic meningitis reported in pediatric and adult patients. (5.6)
- Medication errors involving LAMICTAL have occurred. In particular the names LAMICTAL or lamotrigine can be confused with names of other commonly used medications. Medication errors may also occur between the different formulations of LAMICTAL. (3.4, 5.7, 16, 17.10)

6 ADVERSE REACTIONS

- Most common adverse reactions (incidence ≥10%) in adult epilepsy clinical studies were dizziness, headache, diplopia, ataxia, nausea, blurred vision, somnolence, rhinitis, and rash. Additional adverse reactions (incidence ≥10%) reported in children in epilepsy clinical studies included vomiting, infection, fever, accidental injury, pharyngitis, abdominal pain, and tremor. (6.1)
- Most common adverse reactions (incidence >5%) in adult bipolar clinical studies were nausea, insomnia, somnolence, back pain, fatigue, rash, rhinitis, abdominal pain, and xerostomia. (6.1)

To report SUSPECTED ADVERSE REACTIONS, contact GlaxoSmithKline at 1-888-825-5249 or FDA at 1-800-FDA-1088 or www.fda.gov/medwatch.

7 DRUG INTERACTIONS

- Valproate increases lamotrigine concentrations more than 2-fold. (7, 12.3)
- Carbamazepine, phenytoin, phenobarbital, and primidone decrease lamotrigine concentrations by approximately 40%. (7, 12.3)
- Oral estrogen-containing contraceptives and rifampin also decrease lamotrigine concentrations by approximately 50%. (7, 12.3)

8 USE IN SPECIFIC POPULATIONS

- Hepatic impairment: Dosage adjustments required. (2.1)
- Healthcare professionals can enroll patients in the Lamotrigine Pregnancy Registry (1-800-336-2176). Patients can enroll themselves in the North American Antiepileptic Drug Pregnancy Registry (1-888-233-2334). (8.1)
- Efficacy of LAMICTAL, used as adjunctive treatment for partial seizures, was not demonstrated in a small randomized, double-blind, placebo-controlled study in very young pediatric patients (1 to 24 months). (8.4)

FULL PRESCRIBING INFORMATION

WARNING: SERIOUS SKIN RASHES

LAMICTAL® can cause serious rashes requiring hospitalization and discontinuation of treatment. The incidence of these rashes, which have included Stevens-Johnson syndrome, is approximately 0.8% (8 per 1,000) in pediatric patients (2 to 16 years of age) receiving LAMICTAL as adjunctive therapy for epilepsy and 0.3% (3 per 1,000) in adults on adjunctive therapy for epilepsy. In clinical trials of bipolar and other mood disorders, the rate of serious rash was 0.08% (0.8 per 1,000) in adult patients receiving LAMICTAL as initial monotherapy and 0.13% (1.3 per 1,000) in adult patients receiving LAMICTAL as adjunctive therapy. In a prospectively followed cohort of 1,983 pediatric patients (2 to 16 years of age) with epilepsy taking adjunctive LAMICTAL, there was 1 rash-related death. In worldwide postmarketing experience, rare cases of toxic epidermal necrolysis and/or rash-related death have been reported in adult and pediatric patients, but their numbers are too few to permit a precise estimate of the rate.

Other than age, there are as yet no factors identified that are known to predict the risk of occurrence or the severity of rash caused by LAMICTAL. There are suggestions, yet to be proven, that the risk of rash may also be increased by (1) coadministration of LAMICTAL with valproate (includes valproic acid and divalproex sodium), (2) exceeding the recommended initial dose of LAMICTAL, or (3) exceeding the recommended dose escalation for LAMICTAL. However, cases have occurred in the absence of these factors.

Nearly all cases of life-threatening rashes caused by LAMICTAL have occurred within 2 to 8 weeks of treatment initiation. However, isolated cases have occurred after prolonged treatment (e.g., 6 months). Accordingly, duration of therapy cannot be relied upon as means to predict the potential risk heralded by the first appearance of a rash.

Although benign rashes are also caused by LAMICTAL, it is not possible to predict reliably which rashes will prove to be serious or life threatening. Accordingly, LAMICTAL should ordinarily be discontinued at the first sign of rash, unless the rash is clearly not drug related. Discontinuation of treatment may not prevent a rash from becoming life threatening or permanently disabling or disfiguring [see Warnings and Precautions (5.1)].

1 INDICATIONS AND USAGE

1.1 Epilepsy

Adjunctive Therapy: LAMICTAL is indicated as adjunctive therapy for the following seizure types in patients ≥2 years of age:

- partial seizures
- primary generalized tonic-clonic seizures
- generalized seizures of Lennox-Gastaut syndrome

Monotherapy: LAMICTAL is indicated for conversion to monotherapy in adults (≥16 years of age) with partial seizures who are receiving treatment with carbamazepine, phenytoin, phenobarbital, primidone, or valproate as the single antiepileptic drug (AED).

Safety and effectiveness of LAMICTAL have not been established (1) as initial monotherapy; (2) for conversion to monotherapy from AEDs other than carbamazepine, phenytoin, phenobarbital, primidone, or valproate; or (3) for simultaneous conversion to monotherapy from 2 or more concomitant AEDs.

1.2 Bipolar Disorder

LAMICTAL is indicated for the maintenance treatment of Bipolar I Disorder to delay the time to occurrence of mood episodes (depression, mania, hypomania, mixed episodes) in adults (≥18 years of age) treated for acute mood episodes with standard therapy. The effectiveness of LAMICTAL in the acute treatment of mood episodes has not been established.

The effectiveness of LAMICTAL as maintenance treatment was established in 2 placebo-controlled trials in patients with Bipolar I Disorder as defined by DSM-IV [see Clinical Studies (14.2)]. The physician who elects to prescribe LAMICTAL for periods extending beyond 16 weeks should periodically re-evaluate the long-term usefulness of the drug for the individual patient.

2 DOSAGE AND ADMINISTRATION

2.1 General Dosing Considerations

Rash: There are suggestions, yet to be proven, that the risk of severe, potentially life-threatening rash may be increased by (1) coadministration of LAMICTAL with valproate, (2) exceeding the recommended initial dose of LAMICTAL, or (3) exceeding the recommended dose escalation for LAMICTAL. However, cases have occurred in the absence of these factors [see Boxed Warning]. Therefore, it is important that the dosing recommendations be followed closely.

The risk of nonserious rash may be increased when the recommended initial dose and/or the rate of dose escalation of LAMICTAL is exceeded and in patients with a history of allergy or rash to other AEDs.

LAMICTAL Starter Kits and LAMICTAL® ODT™ Patient Titration Kits provide LAMICTAL at doses consistent with the recommended titration schedule for the first 5 weeks of treatment, based upon concomitant medications for patients with epilepsy (>12 years of age) and Bipolar I Disorder (≥18 years of age) and are intended to help reduce the potential for rash. The use of LAMICTAL Starter Kits and LAMICTAL ODT Patient Titration Kits is recommended for appropriate patients who are starting or restarting LAMICTAL [see How Supplied/Storage and Handling (16)].

It is recommended that LAMICTAL not be restarted in patients who discontinued due to rash associated with prior treatment with lamotrigine, unless the potential benefits clearly outweigh the risks. If the decision is made to restart a patient who has discontinued lamotrigine, the need to restart with the initial dosing recommendations should be assessed. The greater the interval of time since the previous dose, the greater consideration should be given to restarting with the initial dosing recommendations. If a patient has discontinued lamotrigine for a period of more than 5 half-lives, it is recommended that initial dosing recommendations and guidelines be followed. The half-life of lamotrigine is affected by other concomitant medications [see Clinical Pharmacology (12.3)].

LAMICTAL Added to Drugs Known to Induce or Inhibit Glucuronidation: Drugs other than those listed in the Clinical Pharmacology section [see Clinical Pharmacology (12.3)] have not been systematically evaluated in combination with lamotrigine. Because lamotrigine is metabolized predominantly by glucuronic acid conjugation, drugs that are known to induce or inhibit glucuronidation may affect the apparent clearance of lamotrigine and doses of LAMICTAL may require adjustment based on clinical response.

Target Plasma Levels for Patients With Epilepsy or Bipolar Disorder: A therapeutic plasma concentration range has not been established for lamotrigine. Dosing of LAMICTAL should be based on therapeutic response [see Clinical Pharmacology (12.3)].

Women Taking Estrogen-Containing Oral Contraceptives: Starting LAMICTAL in Women Taking Estrogen-Containing Oral Contraceptives: Although estrogen-containing oral contraceptives have been shown to increase the clearance of lamotrigine [see Clinical Pharmacology (12.3)], no adjustments to the recommended dose-escalation guidelines for LAMICTAL should be necessary solely based on the use of estrogen-containing oral contraceptives. Therefore, dose escalation should follow the recommended guidelines for initiating adjunctive therapy with LAMICTAL based on the concomitant AED or other concomitant medications (see Table 1 or Table 5). See below for adjustments to maintenance doses of LAMICTAL in women taking estrogen-containing oral contraceptives.

Adjustments to the Maintenance Dose of LAMICTAL in Women Taking Estrogen-Containing Oral Contraceptives:

(1) Taking Estrogen-Containing Oral Contraceptives: For women not taking carbamazepine, phenytoin, phenobarbital, primidone, or other drugs such as rifampin that induce lamotrigine glucuronidation [see Drug Interactions (7), Clinical Pharmacology (12.3)], the maintenance dose of LAMICTAL will in most cases need to be increased, by as much as 2-fold over the recommended target maintenance dose, in order to maintain a consistent lamotrigine plasma level [see Clinical Pharmacology (12.3)].

(2) Starting Estrogen-Containing Oral Contraceptives: In women taking a stable dose of LAMICTAL and not taking carbamazepine, phenytoin, phenobarbital, primidone, or other drugs such as rifampin that induce lamotrigine glucuronidation [see Drug Interactions (7), Clinical Pharmacology (12.3)], the maintenance dose will in most cases need to be increased by as much as 2-fold in order to maintain a consistent lamotrigine plasma level. The dose increases should begin at the same time that the oral contraceptive is introduced and continue, based on clinical response, no more rapidly than 50 to 100 mg/day every week. Dose increases should not exceed the recommended rate (see Table 1 or Table 5) unless lamotrigine plasma levels or clinical response support larger increases. Gradual transient increases in lamotrigine plasma levels may occur during the week of inactive hormonal preparation (“pill-free” week), and these increases will be greater if dose increases are made in the days before or during the week of inactive hormonal preparation. Increased lamotrigine plasma levels could result in additional adverse reactions, such as dizziness, ataxia, and diplopia. If adverse reactions attributable to LAMICTAL consistently occur during the “pill-free” week, dose adjustments to the overall maintenance dose may be necessary. Dose adjustments limited to the “pill-free” week are not recommended. For women taking LAMICTAL in addition to carbamazepine, phenytoin, phenobarbital, primidone, or other drugs such as rifampin that induce lamotrigine glucuronidation [see Drug Interactions (7), Clinical Pharmacology (12.3)], no adjustment to the dose of LAMICTAL should be necessary.

(3) Stopping Estrogen-Containing Oral Contraceptives: For women not taking carbamazepine, phenytoin, phenobarbital, primidone, or other drugs such as rifampin that induce lamotrigine glucuronidation [see Drug Interactions (7), Clinical Pharmacology (12.3)], the maintenance dose of LAMICTAL will in most cases need to be decreased by as much as 50% in order to maintain a consistent lamotrigine plasma level. The decrease in dose of LAMICTAL should not exceed 25% of the total daily dose per week over a 2-week period, unless clinical response or lamotrigine plasma levels indicate otherwise [see Clinical Pharmacology (12.3)]. For women taking LAMICTAL in addition to carbamazepine, phenytoin, phenobarbital, primidone, or other drugs such as rifampin that induce lamotrigine glucuronidation [see Drug Interactions (7), Clinical Pharmacology (12.3)], no adjustment to the dose of LAMICTAL should be necessary.

Women and Other Hormonal Contraceptive Preparations or Hormone Replacement Therapy: The effect of other hormonal contraceptive preparations or hormone replacement therapy on the pharmacokinetics of lamotrigine has not been systematically evaluated. It has been reported that ethinylestradiol, not progestogens, increased the clearance of lamotrigine up to 2-fold, and the progestin-only pills had no effect on lamotrigine plasma levels. Therefore, adjustments to the dosage of LAMICTAL in the presence of progestogens alone will likely not be needed.

Patients With Hepatic Impairment: Experience in patients with hepatic impairment is limited. Based on a clinical pharmacology study in 24 patients with mild, moderate, and severe liver impairment [see Use in Specific Populations (8.6), Clinical Pharmacology (12.3)], the following general recommendations can be made. No dosage adjustment is needed in patients with mild liver impairment. Initial, escalation, and maintenance doses should generally be reduced by approximately 25% in patients with moderate and severe liver impairment without ascites and 50% in patients with severe liver impairment with ascites. Escalation and maintenance doses may be adjusted according to clinical response.

Patients With Renal Impairment: Initial doses of LAMICTAL should be based on patients’ concomitant medications (see Tables 1-3 or Table 5); reduced maintenance doses may be effective for patients with significant renal impairment [see Use in Specific Populations (8.7), Clinical Pharmacology (12.3)]. Few patients with severe renal impairment have been evaluated during chronic treatment with LAMICTAL. Because there is inadequate experience in this population, LAMICTAL should be used with caution in these patients.

Discontinuation Strategy: Epilepsy: For patients receiving LAMICTAL in combination with other AEDs, a reevaluation of all AEDs in the regimen should be considered if a change in seizure control or an appearance or worsening of adverse reactions is observed.

If a decision is made to discontinue therapy with LAMICTAL, a step-wise reduction of dose over at least 2 weeks (approximately 50% per week) is recommended unless safety concerns require a more rapid withdrawal [see Warnings and Precautions (5.9)].

Discontinuing carbamazepine, phenytoin, phenobarbital, primidone, or other drugs such as rifampin that induce lamotrigine glucuronidation should prolong the half-life of lamotrigine; discontinuing valproate should shorten the half-life of lamotrigine.

Bipolar Disorder: In the controlled clinical trials, there was no increase in the incidence, type, or severity of adverse reactions following abrupt termination of LAMICTAL. In clinical trials in patients with Bipolar Disorder, 2 patients experienced seizures shortly after abrupt withdrawal of LAMICTAL. However, there were confounding factors that may have contributed to the occurrence of seizures in these bipolar patients. Discontinuation of LAMICTAL should involve a step-wise reduction of dose over at least 2 weeks (approximately 50% per week) unless safety concerns require a more rapid withdrawal [see Warnings and Precautions (5.9)].

2.2 Epilepsy – Adjunctive Therapy

This section provides specific dosing recommendations for patients greater than 12 years of age and patients 2 to 12 years of age. Within each of these age-groups, specific dosing recommendations are provided depending upon concomitant AED or other concomitant medications (Table 1 for patients greater than 12 years of age and Table 2 for patients 2 to 12 years of age). A weight-based dosing guide for patients 2 to 12 years of age on concomitant valproate is provided in Table 3.

Patients Over 12 Years of Age: Recommended dosing guidelines are summarized in Table 1.

Table 1. Escalation Regimen for LAMICTAL in Patients Over 12 Years of Age With Epilepsy
 | For Patients TAKING Valproatea | For Patients NOT TAKING Carbamazepine, Phenytoin, Phenobarbital, Primidone,b or Valproatea | For Patients TAKING Carbamazepine, Phenytoin, Phenobarbital, or Primidoneb and NOT TAKING Valproatea
Weeks 1 and 2 | 25 mg every other day | 25 mg every day | 50 mg/day
Weeks 3 and 4 | 25 mg every day | 50 mg/day | 100 mg/day; (in 2 divided doses)
Week 5 onwards to maintenance | Increase by 25 to 50 mg/day every 1 to 2 weeks | Increase by 50 mg/day every 1 to 2 weeks | Increase by 100 mg/day every 1 to 2 weeks.
Usual maintenance dose | 100 to 200 mg/day with valproate alone; 100 to 400 mg/day with valproate and other drugs that induce glucuronidation; (in 1 or 2 divided doses) | 225 to 375 mg/day; (in 2 divided doses) | 300 to 500 mg/day; (in 2 divided doses)

aValproate has been shown to inhibit glucuronidation and decrease the apparent clearance of lamotrigine [see Drug Interactions (7), Clinical Pharmacology (12.3)].

bThese drugs induce lamotrigine glucuronidation and increase clearance [see Drug Interactions (7), Clinical Pharmacology (12.3)]. Other drugs that have similar effects include estrogen-containing oral contraceptives [see Drug Interactions (7), Clinical Pharmacology (12.3)]. Dosing recommendations for oral contraceptives can be found in General Dosing Considerations [see Dosage and Administration (2.1)]. Patients on rifampin, or other drugs that induce lamotrigine glucuronidation and increase clearance, should follow the same dosing titration/maintenance regimen as that used with anticonvulsants that have this effect.

Patients 2 to 12 Years of Age: Recommended dosing guidelines are summarized in Table 2.

Smaller starting doses and slower dose escalations than those used in clinical trials are recommended because of the suggestion that the risk of rash may be decreased by smaller starting doses and slower dose escalations. Therefore, maintenance doses will take longer to reach in clinical practice than in clinical trials. It may take several weeks to months to achieve an individualized maintenance dose. Maintenance doses in patients weighing less than 30 kg, regardless of age or concomitant AED, may need to be increased as much as 50%, based on clinical response.

The smallest available strength of LAMICTAL Chewable Dispersible Tablets is 2 mg, and only whole tablets should be administered. If the calculated dose cannot be achieved using whole tablets, the dose should be rounded down to the nearest whole tablet [see How Supplied/Storage and Handling (16) and Medication Guide].

Table 2. Escalation Regimen for LAMICTAL in Patients 2 to 12 Years of Age With Epilepsy
 | For Patients TAKING Valproatea | For Patients NOT TAKING Carbamazepine, Phenytoin, Phenobarbital, Primidone,b or Valproatea | For Patients TAKING Carbamazepine, Phenytoin, Phenobarbital, or Primidoneb and NOT TAKING Valproatea
Weeks 1 and 2 | 0.15 mg/kg/day; in 1 or 2 divided doses, rounded down to the nearest whole tablet (see Table 3 for weight-based dosing guide) | 0.3 mg/kg/day; in 1 or 2 divided doses, rounded down to the nearest whole tablet | 0.6 mg/kg/day; in 2 divided doses, rounded down to the nearest whole tablet
Weeks 3 and 4 | 0.3 mg/kg/day; in 1 or 2 divided doses, rounded down to the nearest whole tablet (see Table 3 for weight-based dosing guide) | 0.6 mg/kg/day; in 2 divided doses, rounded down to the nearest whole tablet | 1.2 mg/kg/day; in 2 divided doses, rounded down to the nearest whole tablet
Week 5 onwards to maintenance | The dose should be increased every 1 to 2 weeks as follows: calculate 0.3 mg/kg/day, round this amount down to the nearest whole tablet, and add this amount to the previously administered daily dose | The dose should be increased every 1 to 2 weeks as follows: calculate 0.6 mg/kg/day, round this amount down to the nearest whole tablet, and add this amount to the previously administered daily dose | The dose should be increased every 1 to 2 weeks as follows: calculate 1.2 mg/kg/day, round this amount down to the nearest whole tablet, and add this amount to the previously administered daily dose
Usual maintenance dose | 1 to 5 mg/kg/day(maximum 200 mg/day in 1 or 2 divided doses); 1 to 3 mg/kg/day; with valproate alone | 4.5 to 7.5 mg/kg/day; (maximum 300 mg/day in 2 divided doses) | 5 to 15 mg/kg/day; (maximum 400 mg/day in 2 divided doses)
Maintenance dose in patients less than 30 kg | May need to be increased by as much as 50%, based on clinical response | May need to be increased by as much as 50%, based on clinical response | May need to be increased by as much as 50%, based on clinical response

Note: Only whole tablets should be used for dosing.

aValproate has been shown to inhibit glucuronidation and decrease the apparent clearance of lamotrigine [see Drug Interactions (7), Clinical Pharmacology (12.3)].

bThese drugs induce lamotrigine glucuronidation and increase clearance [see Drug Interactions (7), Clinical Pharmacology (12.3)]. Other drugs that have similar effects include estrogen-containing oral contraceptives [see Drug Interactions (7), Clinical Pharmacology (12.3)]. Dosing recommendations for oral contraceptives can be found in General Dosing Considerations [see Dosage and Administration (2.1)]. Patients on rifampin, or other drugs that induce lamotrigine glucuronidation and increase clearance, should follow the same dosing titration/maintenance regimen as that used with anticonvulsants that have this effect.

Table 3. The Initial Weight-Based Dosing Guide for Patients 2 to 12 Years of Age Taking Valproate (Weeks 1 to 4) With Epilepsy
If the patient’s weight is |  | Give this daily dose, using the most appropriate combination of LAMICTAL 2-mg and 5-mg tablets
Greater than | And less than | Weeks 1 and 2 | Weeks 3 and 4
6.7 kg | 14 kg | 2 mg every other day | 2 mg every day
14.1 kg | 27 kg | 2 mg every day | 4 mg every day
27.1 kg | 34 kg | 4 mg every day | 8 mg every day
34.1 kg | 40 kg | 5 mg every day | 10 mg every day

Usual Adjunctive Maintenance Dose for Epilepsy: The usual maintenance doses identified in Tables 1 and 2 are derived from dosing regimens employed in the placebo-controlled adjunctive studies in which the efficacy of LAMICTAL was established. In patients receiving multidrug regimens employing carbamazepine, phenytoin, phenobarbital, or primidone without valproate, maintenance doses of adjunctive LAMICTAL as high as 700 mg/day have been used. In patients receiving valproate alone, maintenance doses of adjunctive LAMICTAL as high as 200 mg/day have been used. The advantage of using doses above those recommended in Tables 1 through 4 has not been established in controlled trials.

2.3 Epilepsy – Conversion From Adjunctive Therapy to Monotherapy

The goal of the transition regimen is to effect the conversion to monotherapy with LAMICTAL under conditions that ensure adequate seizure control while mitigating the risk of serious rash associated with the rapid titration of LAMICTAL.

The recommended maintenance dose of LAMICTAL as monotherapy is 500 mg/day given in 2 divided doses.

To avoid an increased risk of rash, the recommended initial dose and subsequent dose escalations of LAMICTAL should not be exceeded [see Boxed Warning].

Conversion From Adjunctive Therapy With Carbamazepine, Phenytoin, Phenobarbital, or Primidone to Monotherapy With LAMICTAL: After achieving a dose of 500 mg/day of LAMICTAL according to the guidelines in Table 1, the concomitant AED should be withdrawn by 20% decrements each week over a 4-week period. The regimen for the withdrawal of the concomitant AED is based on experience gained in the controlled monotherapy clinical trial.

Conversion From Adjunctive Therapy With Valproate to Monotherapy With LAMICTAL: The conversion regimen involves 4 steps outlined in Table 4.

Table 4. Conversion From Adjunctive Therapy With Valproate to Monotherapy With LAMICTAL in Patients ≥16 Years of Age With Epilepsy
 | LAMICTAL | Valproate
Step 1 | Achieve a dose of 200 mg/day according to guidelines in Table 1 (if not already on 200 mg/day). | Maintain previous stable dose.
Step 2 | Maintain at 200 mg/day. | Decrease to 500 mg/day by decrements no greater than 500 mg/day/week and then maintain the dose of 500 mg/day for 1 week.
Step 3 | Increase to 300 mg/day and maintain for 1 week. | Simultaneously decrease to 250 mg/day and maintain for 1 week.
Step 4 | Increase by 100 mg/day every week to achieve maintenance dose of 500 mg/day. | Discontinue.

Conversion From Adjunctive Therapy With Antiepileptic Drugs Other Than Carbamazepine, Phenytoin, Phenobarbital, Primidone, or Valproate to Monotherapy With LAMICTAL: No specific dosing guidelines can be provided for conversion to monotherapy with LAMICTAL with AEDs other than carbamazepine, phenobarbital, phenytoin, primidone, or valproate.

2.4 Bipolar Disorder

The goal of maintenance treatment with LAMICTAL is to delay the time to occurrence of mood episodes (depression, mania, hypomania, mixed episodes) in patients treated for acute mood episodes with standard therapy. The target dose of LAMICTAL is 200 mg/day (100 mg/day in patients taking valproate, which decreases the apparent clearance of lamotrigine, and 400 mg/day in patients not taking valproate and taking either carbamazepine, phenytoin, phenobarbital, primidone, or other drugs such as rifampin that increase the apparent clearance of lamotrigine). In the clinical trials, doses up to 400 mg/day as monotherapy were evaluated; however, no additional benefit was seen at 400 mg/day compared with 200 mg/day [see Clinical Studies (14.2)]. Accordingly, doses above 200 mg/day are not recommended. Treatment with LAMICTAL is introduced, based on concurrent medications, according to the regimen outlined in Table 5. If other psychotropic medications are withdrawn following stabilization, the dose of LAMICTAL should be adjusted. For patients discontinuing valproate, the dose of LAMICTAL should be doubled over a 2-week period in equal weekly increments (see Table 6). For patients discontinuing carbamazepine, phenytoin, phenobarbital, primidone, or other drugs such as rifampin that induce lamotrigine glucuronidation, the dose of LAMICTAL should remain constant for the first week and then should be decreased by half over a 2-week period in equal weekly decrements (see Table 6). The dose of LAMICTAL may then be further adjusted to the target dose (200 mg) as clinically indicated.

If other drugs are subsequently introduced, the dose of LAMICTAL may need to be adjusted. In particular, the introduction of valproate requires reduction in the dose of LAMICTAL [see Drug Interactions (7), Clinical Pharmacology (12.3)].

To avoid an increased risk of rash, the recommended initial dose and subsequent dose escalations of LAMICTAL should not be exceeded [see Boxed Warning].

Table 5. Escalation Regimen for LAMICTAL for Patients With Bipolar Disorder
 | For Patients TAKING Valproatea | For Patients NOT TAKING Carbamazepine, Phenytoin, Phenobarbital, Primidone,b or Valproatea | For Patients TAKING Carbamazepine, Phenytoin, Phenobarbital, or Primidoneb and NOT TAKING Valproatea
Weeks 1 and 2 | 25 mg every other day | 25 mg daily | 50 mg daily
Weeks 3 and 4 | 25 mg daily | 50 mg daily | 100 mg daily, in divided doses
Week 5 | 50 mg daily | 100 mg daily | 200 mg daily, in divided doses
Week 6 | 100 mg daily | 200 mg daily | 300 mg daily, in divided doses
Week 7 | 100 mg daily | 200 mg daily | up to 400 mg daily, in divided doses

aValproate has been shown to inhibit glucuronidation and decrease the apparent clearance of lamotrigine [see Drug Interactions (7), Clinical Pharmacology (12.3)].

bThese drugs induce lamotrigine glucuronidation and increase clearance [see Drug Interactions (7), Clinical Pharmacology (12.3)]. Other drugs that have similar effects include estrogen-containing oral contraceptives [see Drug Interactions (7), Clinical Pharmacology (12.3)]. Dosing recommendations for oral contraceptives can be found in General Dosing Considerations [see Dosage and Administration (2.1)]. Patients on rifampin, or other drugs that induce lamotrigine glucuronidation and increase clearance, should follow the same dosing titration/maintenance regimen as that used with anticonvulsants that have this effect.

Table 6. Dosage Adjustments to LAMICTAL for Patients With Bipolar Disorder Following Discontinuation of Psychotropic Medications
 | Discontinuation of Psychotropic Drugs (excluding Carbamazepine, Phenytoin, Phenobarbital, Primidone,b or Valproatea) | After Discontinuation of Valproatea | After Discontinuation of Carbamazepine, Phenytoin, Phenobarbital, or Primidoneb
 | Discontinuation of Psychotropic Drugs (excluding Carbamazepine, Phenytoin, Phenobarbital, Primidone,b or Valproatea) | Current dose of LAMICTAL (mg/day); 100 | Current dose of LAMICTAL (mg/day); 400
Week 1 | Maintain current dose of LAMICTAL | 150 | 400
Week 2 | Maintain current dose of LAMICTAL | 200 | 300
Week 3 onward | Maintain current dose of LAMICTAL | 200 | 200

aValproate has been shown to inhibit glucuronidation and decrease the apparent clearance of lamotrigine [see Drug Interactions (7), Clinical Pharmacology (12.3)].

bThese drugs induce lamotrigine glucuronidation and increase clearance [see Drug Interactions (7), Clinical Pharmacology (12.3)]. Other drugs that have similar effects include estrogen-containing oral contraceptives [see Drug Interactions (7), Clinical Pharmacology (12.3)]. Dosing recommendations for oral contraceptives can be found in General Dosing Considerations [see Dosage and Administration (2.1)]. Patients on rifampin, or other drugs that induce lamotrigine glucuronidation and increase clearance, should follow the same dosing titration/maintenance regimen as that used with anticonvulsants that have this effect.

The benefit of continuing treatment in patients who had been stabilized in an 8- to 16-week open-label phase with LAMICTAL was established in 2 randomized, placebo-controlled clinical maintenance trials [see Clinical Studies (14.2)]. However, the optimal duration of treatment with LAMICTAL has not been established. Thus, patients should be periodically reassessed to determine the need for maintenance treatment.

2.5 Administration of LAMICTAL Chewable Dispersible Tablets

LAMICTAL Chewable Dispersible Tablets may be swallowed whole, chewed, or dispersed in water or diluted fruit juice. If the tablets are chewed, consume a small amount of water or diluted fruit juice to aid in swallowing.

To disperse LAMICTAL Chewable Dispersible Tablets, add the tablets to a small amount of liquid (1 teaspoon, or enough to cover the medication). Approximately 1 minute later, when the tablets are completely dispersed, swirl the solution and consume the entire quantity immediately. No attempt should be made to administer partial quantities of the dispersed tablets.

2.6 Administration of LAMICTAL ODT Orally Disintegrating Tablets

LAMICTAL ODT Orally Disintegrating Tablets should be placed onto the tongue and moved around in the mouth. The tablet will disintegrate rapidly, can be swallowed with or without water, and can be taken with or without food.

3 DOSAGE FORMS AND STRENGTHS

3.1 Tablets

25 mg, white, scored, shield-shaped tablets debossed with “LAMICTAL” and “25.”

100 mg, peach, scored, shield-shaped tablets debossed with “LAMICTAL” and “100.”

150 mg, cream, scored, shield-shaped tablets debossed with “LAMICTAL” and “150.”

200 mg, blue, scored, shield-shaped tablets debossed with “LAMICTAL” and “200.”

3.2 Chewable Dispersible Tablets

2 mg, white to off-white, round tablets debossed with “LTG” over “2.”

5 mg, white to off-white, caplet-shaped tablets debossed with “GX CL2.”

25 mg, white, super elliptical-shaped tablets debossed with “GX CL5.”

3.3 Orally Disintegrating Tablets

25 mg, white to off-white, round, flat-faced, radius edge, tablets debossed with “LMT” on one side and “25” on the other side.

50 mg, white to off-white, round, flat-faced, radius edge, tablets debossed with “LMT” on one side and “50” on the other side.

100 mg, white to off-white, round, flat-faced, radius edge, tablets debossed with “LAMICTAL” on one side and “100” on the other side.

200 mg, white to off-white, round, flat-faced, radius edge, tablets debossed with “LAMICTAL” on one side and “200” on the other side.

3.4 Potential Medication Errors

Patients should be strongly advised to visually inspect their tablets to verify that they are receiving LAMICTAL as well as the correct formulation of LAMICTAL each time they fill their prescription. Depictions of the LAMICTAL Tablets, Chewable Dispersible Tablets, and Orally Disintegrating Tablets can be found in the Medication Guide that accompanies the product.

4 CONTRAINDICATIONS

LAMICTAL is contraindicated in patients who have demonstrated hypersensitivity to the drug or its ingredients [see Boxed Warning, Warnings and Precautions (5.1, 5.2)].

5 WARNINGS AND PRECAUTIONS

5.1 Serious Skin Rashes [see Boxed Warning]

Pediatric Population: The incidence of serious rash associated with hospitalization and discontinuation of LAMICTAL in a prospectively followed cohort of pediatric patients (2 to 16 years of age) with epilepsy receiving adjunctive therapy was approximately 0.8% (16 of 1,983). When 14 of these cases were reviewed by 3 expert dermatologists, there was considerable disagreement as to their proper classification. To illustrate, one dermatologist considered none of the cases to be Stevens-Johnson syndrome; another assigned 7 of the 14 to this diagnosis. There was 1 rash-related death in this 1,983-patient cohort. Additionally, there have been rare cases of toxic epidermal necrolysis with and without permanent sequelae and/or death in US and foreign postmarketing experience.

There is evidence that the inclusion of valproate in a multidrug regimen increases the risk of serious, potentially life-threatening rash in pediatric patients. In pediatric patients who used valproate concomitantly, 1.2% (6 of 482) experienced a serious rash compared with 0.6% (6 of 952) patients not taking valproate.

Adult Population: Serious rash associated with hospitalization and discontinuation of LAMICTAL occurred in 0.3% (11 of 3,348) of adult patients who received LAMICTAL in premarketing clinical trials of epilepsy. In the bipolar and other mood disorders clinical trials, the rate of serious rash was 0.08% (1 of 1,233) of adult patients who received LAMICTAL as initial monotherapy and 0.13% (2 of 1,538) of adult patients who received LAMICTAL as adjunctive therapy. No fatalities occurred among these individuals. However, in worldwide postmarketing experience, rare cases of rash-related death have been reported, but their numbers are too few to permit a precise estimate of the rate.

Among the rashes leading to hospitalization were Stevens-Johnson syndrome, toxic epidermal necrolysis, angioedema, and those associated with multiorgan hypersensitivity [see Warnings and Precautions (5.2)].

There is evidence that the inclusion of valproate in a multidrug regimen increases the risk of serious, potentially life-threatening rash in adults. Specifically, of 584 patients administered LAMICTAL with valproate in epilepsy clinical trials, 6 (1%) were hospitalized in association with rash; in contrast, 4 (0.16%) of 2,398 clinical trial patients and volunteers administered LAMICTAL in the absence of valproate were hospitalized.

Patients With History of Allergy or Rash to Other Antiepileptic Drugs: The risk of nonserious rash may be increased when the recommended initial dose and/or the rate of dose escalation of LAMICTAL is exceeded and in patients with a history of allergy or rash to other AEDs.

5.2 Multiorgan Hypersensitivity Reactions and Organ Failure

Multiorgan hypersensitivity reactions, also known as Drug Reaction with Eosinophilia and Systemic Symptoms (DRESS), have occurred with LAMICTAL. Some have been fatal or life threatening. DRESS typically, although not exclusively, presents with fever, rash, and/or lymphadenopathy in association with other organ system involvement, such as hepatitis, nephritis, hematologic abnormalities, myocarditis, or myositis, sometimes resembling an acute viral infection. Eosinophilia is often present. This disorder is variable in its expression, and other organ systems not noted here may be involved.

Fatalities associated with acute multiorgan failure and various degrees of hepatic failure have been reported in 2 of 3,796 adult patients and 4 of 2,435 pediatric patients who received LAMICTAL in epilepsy clinical trials. Rare fatalities from multiorgan failure have also been reported in postmarketing use.

Isolated liver failure without rash or involvement of other organs has also been reported with LAMICTAL.

It is important to note that early manifestations of hypersensitivity (e.g., fever, lymphadenopathy) may be present even though a rash is not evident. If such signs or symptoms are present, the patient should be evaluated immediately. LAMICTAL should be discontinued if an alternative etiology for the signs or symptoms cannot be established.

Prior to initiation of treatment with LAMICTAL, the patient should be instructed that a rash or other signs or symptoms of hypersensitivity (e.g., fever, lymphadenopathy) may herald a serious medical event and that the patient should report any such occurrence to a physician immediately.

5.3 Blood Dyscrasias

There have been reports of blood dyscrasias that may or may not be associated with multiorgan hypersensitivity (also known as DRESS) [see Warnings and Precautions (5.2)]. These have included neutropenia, leukopenia, anemia, thrombocytopenia, pancytopenia, and, rarely, aplastic anemia and pure red cell aplasia.

5.4 Suicidal Behavior and Ideation

Antiepileptic drugs (AEDs), including LAMICTAL, increase the risk of suicidal thoughts or behavior in patients taking these drugs for any indication. Patients treated with any AED for any indication should be monitored for the emergence or worsening of depression, suicidal thoughts or behavior, and/or any unusual changes in mood or behavior.

Pooled analyses of 199 placebo-controlled clinical trials (mono- and adjunctive therapy) of 11 different AEDs showed that patients randomized to one of the AEDs had approximately twice the risk (adjusted Relative Risk 1.8, 95% CI:1.2, 2.7) of suicidal thinking or behavior compared to patients randomized to placebo. In these trials, which had a median treatment duration of 12 weeks, the estimated incidence of suicidal behavior or ideation among 27,863 AED-treated patients was 0.43%, compared to 0.24% among 16,029 placebo-treated patients, representing an increase of approximately 1 case of suicidal thinking or behavior for every 530 patients treated. There were 4 suicides in drug-treated patients in the trials and none in placebo-treated patients, but the number of events is too small to allow any conclusion about drug effect on suicide.

The increased risk of suicidal thoughts or behavior with AEDs was observed as early as 1 week after starting treatment with AEDs and persisted for the duration of treatment assessed. Because most trials included in the analysis did not extend beyond 24 weeks, the risk of suicidal thoughts or behavior beyond 24 weeks could not be assessed.

The risk of suicidal thoughts or behavior was generally consistent among drugs in the data analyzed. The finding of increased risk with AEDs of varying mechanism of action and across a range of indications suggests that the risk applies to all AEDs used for any indication. The risk did not vary substantially by age (5 to 100 years) in the clinical trials analyzed.

Table 7 shows absolute and relative risk by indication for all evaluated AEDs.

Table 7. Risk by Indication for Antiepileptic Drugs in the Pooled Analysis
Indication | Placebo Patients With Events Per 1,000 Patients | Drug Patients With Events Per 1,000 Patients | Relative Risk: Incidence of Events in Drug Patients/Incidence in Placebo Patients | Risk Difference: Additional Drug Patients With Events Per 1,000 Patients
Epilepsy | 1.0 | 3.4 | 3.5 | 2.4
Psychiatric | 5.7 | 8.5 | 1.5 | 2.9
Other | 1.0 | 1.8 | 1.9 | 0.9
Total | 2.4 | 4.3 | 1.8 | 1.9

The relative risk for suicidal thoughts or behavior was higher in clinical trials for epilepsy than in clinical trials for psychiatric or other conditions, but the absolute risk differences were similar for the epilepsy and psychiatric indications.

Anyone considering prescribing LAMICTAL or any other AED must balance the risk of suicidal thoughts or behavior with the risk of untreated illness. Epilepsy and many other illnesses for which AEDs are prescribed are themselves associated with morbidity and mortality and an increased risk of suicidal thoughts and behavior. Should suicidal thoughts and behavior emerge during treatment, the prescriber needs to consider whether the emergence of these symptoms in any given patient may be related to the illness being treated.

Patients, their caregivers, and families should be informed that AEDs increase the risk of suicidal thoughts and behavior and should be advised of the need to be alert for the emergence or worsening of the signs and symptoms of depression, any unusual changes in mood or behavior, or the emergence of suicidal thoughts, behavior, or thoughts about self-harm. Behaviors of concern should be reported immediately to healthcare providers.

5.5 Use in Patients With Bipolar Disorder

Acute Treatment of Mood Episodes: Safety and effectiveness of LAMICTAL in the acute treatment of mood episodes have not been established.

Children and Adolescents (less than 18 years of age): Safety and effectiveness of LAMICTAL in patients below the age of 18 years with mood disorders have not been established [see Suicidal Behavior and Ideation (5.4)].

Clinical Worsening and Suicide Risk Associated With Bipolar Disorder: Patients with bipolar disorder may experience worsening of their depressive symptoms and/or the emergence of suicidal ideation and behaviors (suicidality) whether or not they are taking medications for bipolar disorder. Patients should be closely monitored for clinical worsening (including development of new symptoms) and suicidality, especially at the beginning of a course of treatment or at the time of dose changes.

In addition, patients with a history of suicidal behavior or thoughts, those patients exhibiting a significant degree of suicidal ideation prior to commencement of treatment, and young adults are at an increased risk of suicidal thoughts or suicide attempts, and should receive careful monitoring during treatment [see Suicidal Behavior and Ideation (5.5)].

Consideration should be given to changing the therapeutic regimen, including possibly discontinuing the medication, in patients who experience clinical worsening (including development of new symptoms) and/or the emergence of suicidal ideation/behavior especially if these symptoms are severe, abrupt in onset, or were not part of the patient’s presenting symptoms.

Prescriptions for LAMICTAL should be written for the smallest quantity of tablets consistent with good patient management in order to reduce the risk of overdose. Overdoses have been reported for LAMICTAL, some of which have been fatal [see Overdosage (10.1)].

5.6 Aseptic Meningitis

Therapy with LAMICTAL increases the risk of developing aseptic meningitis. Because of the potential for serious outcomes of untreated meningitis due to other causes, patients should also be evaluated for other causes of meningitis and treated as appropriate.

Postmarketing cases of aseptic meningitis have been reported in pediatric and adult patients taking LAMICTAL for various indications. Symptoms upon presentation have included headache, fever, nausea, vomiting, and nuchal rigidity. Rash, photophobia, myalgia, chills, altered consciousness, and somnolence were also noted in some cases. Symptoms have been reported to occur within 1 day to one and a half months following the initiation of treatment. In most cases, symptoms were reported to resolve after discontinuation of LAMICTAL. Re-exposure resulted in a rapid return of symptoms (from within 30 minutes to 1 day following re-initiation of treatment) that were frequently more severe. Some of the patients treated with LAMICTAL who developed aseptic meningitis had underlying diagnoses of systemic lupus erythematosus or other autoimmune diseases.

Cerebrospinal fluid (CSF) analyzed at the time of clinical presentation in reported cases was characterized by a mild-to-moderate pleocytosis, normal glucose levels, and mild-to-moderate increase in protein. CSF white blood cell count differentials showed a predominance of neutrophils in a majority of the cases, although a predominance of lymphocytes was reported in approximately one third of the cases. Some patients also had new onset of signs and symptoms of involvement of other organs (predominantly hepatic and renal involvement), which may suggest that in these cases the aseptic meningitis observed was part of a hypersensitivity reaction [see Warnings and Precautions (5.2)].

5.7 Potential Medication Errors

Medication errors involving LAMICTAL have occurred. In particular, the names LAMICTAL or lamotrigine can be confused with the names of other commonly used medications. Medication errors may also occur between the different formulations of LAMICTAL. To reduce the potential of medication errors, write and say LAMICTAL clearly. Depictions of the LAMICTAL Tablets, Chewable Dispersible Tablets, and Orally Disintegrating Tablets can be found in the Medication Guide that accompanies the product to highlight the distinctive markings, colors, and shapes that serve to identify the different presentations of the drug and thus may help reduce the risk of medication errors. To avoid the medication error of using the wrong drug or formulation, patients should be strongly advised to visually inspect their tablets to verify that they are LAMICTAL, as well as the correct formulation of LAMICTAL, each time they fill their prescription.

5.8 Concomitant Use With Oral Contraceptives

Some estrogen-containing oral contraceptives have been shown to decrease serum concentrations of lamotrigine [see Clinical Pharmacology (12.3)]. Dosage adjustments will be necessary in most patients who start or stop estrogen-containing oral contraceptives while taking LAMICTAL [see Dosage and Administration (2.1)]. During the week of inactive hormone preparation (“pill-free” week) of oral contraceptive therapy, plasma lamotrigine levels are expected to rise, as much as doubling at the end of the week. Adverse reactions consistent with elevated levels of lamotrigine, such as dizziness, ataxia, and diplopia, could occur.

5.9 Withdrawal Seizures

As with other AEDs, LAMICTAL should not be abruptly discontinued. In patients with epilepsy there is a possibility of increasing seizure frequency. In clinical trials in patients with Bipolar Disorder, 2 patients experienced seizures shortly after abrupt withdrawal of LAMICTAL; however, there were confounding factors that may have contributed to the occurrence of seizures in these bipolar patients. Unless safety concerns require a more rapid withdrawal, the dose of LAMICTAL should be tapered over a period of at least 2 weeks (approximately 50% reduction per week) [see Dosage and Administration (2.1)].

5.10 Status Epilepticus

Valid estimates of the incidence of treatment-emergent status epilepticus among patients treated with LAMICTAL are difficult to obtain because reporters participating in clinical trials did not all employ identical rules for identifying cases. At a minimum, 7 of 2,343 adult patients had episodes that could unequivocally be described as status epilepticus. In addition, a number of reports of variably defined episodes of seizure exacerbation (e.g., seizure clusters, seizure flurries) were made.

5.11 Sudden Unexplained Death in Epilepsy (SUDEP)

During the premarketing development of LAMICTAL, 20 sudden and unexplained deaths were recorded among a cohort of 4,700 patients with epilepsy (5,747 patient-years of exposure).

Some of these could represent seizure-related deaths in which the seizure was not observed, e.g., at night. This represents an incidence of 0.0035 deaths per patient-year. Although this rate exceeds that expected in a healthy population matched for age and sex, it is within the range of estimates for the incidence of sudden unexplained deaths in patients with epilepsy not receiving LAMICTAL (ranging from 0.0005 for the general population of patients with epilepsy, to 0.004 for a recently studied clinical trial population similar to that in the clinical development program for LAMICTAL, to 0.005 for patients with refractory epilepsy). Consequently, whether these figures are reassuring or suggest concern depends on the comparability of the populations reported upon to the cohort receiving LAMICTAL and the accuracy of the estimates provided. Probably most reassuring is the similarity of estimated SUDEP rates in patients receiving LAMICTAL and those receiving other AEDs, chemically unrelated to each other, that underwent clinical testing in similar populations. Importantly, that drug is chemically unrelated to LAMICTAL. This evidence suggests, although it certainly does not prove, that the high SUDEP rates reflect population rates, not a drug effect.

5.12 Addition of LAMICTAL to a Multidrug Regimen That Includes Valproate

Because valproate reduces the clearance of lamotrigine, the dosage of lamotrigine in the presence of valproate is less than half of that required in its absence.

5.13 Binding in the Eye and Other Melanin-Containing Tissues

Because lamotrigine binds to melanin, it could accumulate in melanin-rich tissues over time. This raises the possibility that lamotrigine may cause toxicity in these tissues after extended use. Although ophthalmological testing was performed in one controlled clinical trial, the testing was inadequate to exclude subtle effects or injury occurring after long-term exposure. Moreover, the capacity of available tests to detect potentially adverse consequences, if any, of lamotrigine's binding to melanin is unknown [see Clinical Pharmacology (12.2)].

Accordingly, although there are no specific recommendations for periodic ophthalmological monitoring, prescribers should be aware of the possibility of long-term ophthalmologic effects.

5.14 Laboratory Tests

The value of monitoring plasma concentrations of lamotrigine in patients treated with LAMICTAL has not been established. Because of the possible pharmacokinetic interactions between lamotrigine and other drugs including AEDs (see Table 15), monitoring of the plasma levels of lamotrigine and concomitant drugs may be indicated, particularly during dosage adjustments. In general, clinical judgment should be exercised regarding monitoring of plasma levels of lamotrigine and other drugs and whether or not dosage adjustments are necessary.

6 ADVERSE REACTIONS

The following adverse reactions are described in more detail in the Warnings and Precautions section of the label:

- Serious skin rashes [see Warnings and Precautions (5.1)]
- Multiorgan hypersensitivity reactions and organ failure [see Warnings and Precautions (5.2)]
- Blood dyscrasias [see Warnings and Precautions (5.3)]
- Suicidal behaviorand ideation [see Warnings and Precautions (5.4)]
- Aseptic meningitis [see Warnings and Precautions (5.6)]
- Withdrawal seizures [see Warnings and Precautions (5.9)]
- Status epilepticus [see Warnings and Precautions (5.10)]
- Sudden unexplained death in epilepsy [see Warnings and Precautions (5.11)]

6.1 Clinical Trials

Because clinical trials are conducted under widely varying conditions, adverse reaction rates observed in the clinical trials of a drug cannot be directly compared with rates in the clinical trials of another drug and may not reflect the rates observed in practice.

LAMICTAL has been evaluated for safety in patients with epilepsy and in patients with Bipolar I Disorder. Adverse reactions reported for each of these patient populations are provided below. Excluded are adverse reactions considered too general to be informative and those not reasonably attributable to the use of the drug.

Epilepsy: Most Common Adverse Reactions in All Clinical Studies: Adjunctive Therapy in Adults With Epilepsy: The most commonly observed (≥5% for LAMICTAL and more common on drug than placebo) adverse reactions seen in association with LAMICTAL during adjunctive therapy in adults and not seen at an equivalent frequency among placebo-treated patients were: dizziness, ataxia, somnolence, headache, diplopia, blurred vision, nausea, vomiting, and rash. Dizziness, diplopia, ataxia, blurred vision, nausea, and vomiting were dose-related. Dizziness, diplopia, ataxia, and blurred vision occurred more commonly in patients receiving carbamazepine with LAMICTAL than in patients receiving other AEDs with LAMICTAL. Clinical data suggest a higher incidence of rash, including serious rash, in patients receiving concomitant valproate than in patients not receiving valproate [see Warnings and Precautions (5.1)].

Approximately 11% of the 3,378 adult patients who received LAMICTAL as adjunctive therapy in premarketing clinical trials discontinued treatment because of an adverse reaction. The adverse reactions most commonly associated with discontinuation were rash (3.0%), dizziness (2.8%), and headache (2.5%).

In a dose-response study in adults, the rate of discontinuation of LAMICTAL for dizziness, ataxia, diplopia, blurred vision, nausea, and vomiting was dose-related.

Monotherapy in Adults With Epilepsy: The most commonly observed (≥5% for LAMICTAL and more common on drug than placebo) adverse reactions seen in association with the use of LAMICTAL during the monotherapy phase of the controlled trial in adults not seen at an equivalent rate in the control group were vomiting, coordination abnormality, dyspepsia, nausea, dizziness, rhinitis, anxiety, insomnia, infection, pain, weight decrease, chest pain, and dysmenorrhea. The most commonly observed (≥5% for LAMICTAL and more common on drug than placebo) adverse reactions associated with the use of LAMICTAL during the conversion to monotherapy (add-on) period, not seen at an equivalent frequency among low-dose valproate-treated patients, were dizziness, headache, nausea, asthenia, coordination abnormality, vomiting, rash, somnolence, diplopia, ataxia, accidental injury, tremor, blurred vision, insomnia, nystagmus, diarrhea, lymphadenopathy, pruritus, and sinusitis.

Approximately 10% of the 420 adult patients who received LAMICTAL as monotherapy in premarketing clinical trials discontinued treatment because of an adverse reaction. The adverse reactions most commonly associated with discontinuation were rash (4.5%), headache (3.1%), and asthenia (2.4%).

Adjunctive Therapy in Pediatric Patients With Epilepsy: The most commonly observed (≥5% for LAMICTAL and more common on drug than placebo) adverse reactions seen in association with the use of LAMICTAL as adjunctive treatment in pediatric patients 2 to 16 years of age and not seen at an equivalent rate in the control group were infection, vomiting, rash, fever, somnolence, accidental injury, dizziness, diarrhea, abdominal pain, nausea, ataxia, tremor, asthenia, bronchitis, flu syndrome, and diplopia.

In 339 patients 2 to 16 years of age with partial seizures or generalized seizures of Lennox-Gastaut syndrome, 4.2% of patients on LAMICTAL and 2.9% of patients on placebo discontinued due to adverse reactions. The most commonly reported adverse reaction that led to discontinuation of LAMICTAL was rash.

Approximately 11.5% of the 1,081 pediatric patients 2 to 16 years of age who received LAMICTAL as adjunctive therapy in premarketing clinical trials discontinued treatment because of an adverse reaction. The adverse reactions most commonly associated with discontinuation were rash (4.4%), reaction aggravated (1.7%), and ataxia (0.6%).

Controlled Adjunctive Clinical Studies in Adults With Epilepsy: Table 8 lists treatment-emergent adverse reactions that occurred in at least 2% of adult patients with epilepsy treated with LAMICTAL in placebo-controlled trials and were numerically more common in the patients treated with LAMICTAL. In these studies, either LAMICTAL or placebo was added to the patient’s current AED therapy. Adverse reactions were usually mild to moderate in intensity.

Table 8. Treatment-Emergent Adverse Reaction Incidence in Placebo-Controlled Adjunctive Trials in Adult Patients With Epilepsya (Adverse reactions in at least 2% of patients treated with LAMICTAL and numerically more frequent than in the placebo group.)
Body System/Adverse Reaction | Percent of Patients Receiving Adjunctive LAMICTAL; (n = 711) | Percent of Patients Receiving Adjunctive Placebo; (n = 419)
Body as a whole
Headache | 29 | 19
Flu syndrome | 7 | 6
Fever | 6 | 4
Abdominal pain | 5 | 4
Neck pain | 2 | 1
Reaction aggravated; (seizure exacerbation) | 2 | 1
Digestive
Nausea | 19 | 10
Vomiting | 9 | 4
Diarrhea | 6 | 4
Dyspepsia | 5 | 2
Constipation | 4 | 3
Anorexia | 2 | 1
Musculoskeletal
Arthralgia | 2 | 0
Nervous
Dizziness | 38 | 13
Ataxia | 22 | 6
Somnolence | 14 | 7
Incoordination | 6 | 2
Insomnia | 6 | 2
Tremor | 4 | 1
Depression | 4 | 3
Anxiety | 4 | 3
Convulsion | 3 | 1
Irritability | 3 | 2
Speech disorder | 3 | 0
Concentration disturbance | 2 | 1
Respiratory
Rhinitis | 14 | 9
Pharyngitis | 10 | 9
Cough increased | 8 | 6
Skin and appendages
Rash | 10 | 5
Pruritus | 3 | 2
Special senses
Diplopia | 28 | 7
Blurred vision | 16 | 5
Vision abnormality | 3 | 1
Urogenital
Female patients only | (n = 365) | (n = 207)
Dysmenorrhea | 7 | 6
Vaginitis | 4 | 1
Amenorrhea | 2 | 1

aPatients in these adjunctive studies were receiving 1 to 3 of the following concomitant AEDs (carbamazepine, phenytoin, phenobarbital, or primidone) in addition to LAMICTAL or placebo. Patients may have reported multiple adverse reactions during the study or at discontinuation; thus, patients may be included in more than one category.

In a randomized, parallel study comparing placebo and 300 and 500 mg/day of LAMICTAL, some of the more common drug-related adverse reactions were dose-related (see Table 9).

Table 9. Dose-Related Adverse Reactions From a Randomized, Placebo-Controlled Adjunctive Trial in Adults With Epilepsy
Adverse Reaction | Percent of Patients Experiencing Adverse Reactions
Adverse Reaction | Placebo; (n = 73) | LAMICTAL; 300 mg; (n = 71) | LAMICTAL; 500 mg; (n = 72)
Ataxia | 10 | 10 | 28ab
Blurred vision | 10 | 11 | 25ab
Diplopia | 8 | 24a | 49ab
Dizziness | 27 | 31 | 54ab
Nausea | 11 | 18 | 25a
Vomiting | 4 | 11 | 18a

aSignificantly greater than placebo group (P <0.05).

bSignificantly greater than group receiving LAMICTAL 300 mg (P <0.05).

The overall adverse reaction profile for LAMICTAL was similar between females and males, and was independent of age. Because the largest non-Caucasian racial subgroup was only 6% of patients exposed to LAMICTAL in placebo-controlled trials, there are insufficient data to support a statement regarding the distribution of adverse reaction reports by race. Generally, females receiving either LAMICTAL as adjunctive therapy or placebo were more likely to report adverse reactions than males. The only adverse reaction for which the reports on LAMICTAL were greater than 10% more frequent in females than males (without a corresponding difference by gender on placebo) was dizziness (difference = 16.5%). There was little difference between females and males in the rates of discontinuation of LAMICTAL for individual adverse reactions.

Controlled Monotherapy Trial in Adults With Partial Seizures: Table 10 lists treatment-emergent adverse reactions that occurred in at least 5% of patients with epilepsy treated with monotherapy with LAMICTAL in a double-blind trial following discontinuation of either concomitant carbamazepine or phenytoin not seen at an equivalent frequency in the control group.

Table 10. Treatment-Emergent Adverse Reaction Incidence in Adults With Partial Seizures in a Controlled Monotherapy Triala (Adverse reactions in at least 5% of patients treated with LAMICTAL and numerically more frequent than in the valproate group.)
Body System/; Adverse Reaction | Percent of Patients Receiving LAMICTAL as Monotherapyb; (n = 43) | Percent of Patients Receiving Low-Dose Valproatec Monotherapy; (n = 44)
Body as a whole
Pain | 5 | 0
Infection | 5 | 2
Chest pain | 5 | 2
Digestive
Vomiting | 9 | 0
Dyspepsia | 7 | 2
Nausea | 7 | 2
Metabolic and nutritional
Weight decrease | 5 | 2
Nervous
Coordination abnormality | 7 | 0
Dizziness | 7 | 0
Anxiety | 5 | 0
Insomnia | 5 | 2
Respiratory
Rhinitis | 7 | 2
Urogenital (female patients only) | (n = 21) | (n = 28)
Dysmenorrhea | 5 | 0

aPatients in these studies were converted to LAMICTAL or valproate monotherapy from adjunctive therapy with carbamazepine or phenytoin. Patients may have reported multiple adverse reactions during the study; thus, patients may be included in more than one category.

bUp to 500 mg/day.

c1,000 mg/day.

Adverse reactions that occurred with a frequency of less than 5% and greater than 2% of patients receiving LAMICTAL and numerically more frequent than placebo were:

Body as a Whole: Asthenia, fever.

Digestive: Anorexia, dry mouth, rectal hemorrhage, peptic ulcer.

Metabolic and Nutritional: Peripheral edema.

Nervous System: Amnesia, ataxia, depression, hypesthesia, libido increase, decreased reflexes, increased reflexes, nystagmus, irritability, suicidal ideation.

Respiratory: Epistaxis, bronchitis, dyspnea.

Skin and Appendages: Contact dermatitis, dry skin, sweating.

Special Senses: Vision abnormality.

Incidence in Controlled Adjunctive Trials in Pediatric Patients With Epilepsy: Table 11 lists adverse reactions that occurred in at least 2% of 339 pediatric patients with partial seizures or generalized seizures of Lennox-Gastaut syndrome, who received LAMICTAL up to 15 mg/kg/day or a maximum of 750 mg/day. Reported adverse reactions were classified using COSTART terminology.

Table 11. Treatment-Emergent Adverse Reaction Incidence in Placebo-Controlled Adjunctive Trials in Pediatric Patients With Epilepsy (Adverse reactions in at least 2% of patients treated with LAMICTAL and numerically more frequent than in the placebo group.)
Body System/; Adverse Reaction | Percent of Patients Receiving LAMICTAL; (n = 168) | Percent of Patients Receiving Placebo; (n = 171)
Body as a whole
Infection | 20 | 17
Fever | 15 | 14
Accidental injury | 14 | 12
Abdominal pain | 10 | 5
Asthenia | 8 | 4
Flu syndrome | 7 | 6
Pain | 5 | 4
Facial edema | 2 | 1
Photosensitivity | 2 | 0
Cardiovascular
Hemorrhage | 2 | 1
Digestive
Vomiting | 20 | 16
Diarrhea | 11 | 9
Nausea | 10 | 2
Constipation | 4 | 2
Dyspepsia | 2 | 1
Hemic and lymphatic
Lymphadenopathy | 2 | 1
Metabolic and nutritional
Edema | 2 | 0
Nervous system
Somnolence | 17 | 15
Dizziness | 14 | 4
Ataxia | 11 | 3
Tremor | 10 | 1
Emotional lability | 4 | 2
Gait abnormality | 4 | 2
Thinking abnormality | 3 | 2
Convulsions | 2 | 1
Nervousness | 2 | 1
Vertigo | 2 | 1
Respiratory
Pharyngitis | 14 | 11
Bronchitis | 7 | 5
Increased cough | 7 | 6
Sinusitis | 2 | 1
Bronchospasm | 2 | 1
Skin
Rash | 14 | 12
Eczema | 2 | 1
Pruritus | 2 | 1
Special senses
Diplopia | 5 | 1
Blurred vision | 4 | 1
Visual abnormality | 2 | 0
Urogenital
Male and female patients
Urinary tract infection | 3 | 0

Bipolar Disorder: The most commonly observed (≥5%) treatment-emergent adverse reactions seen in association with the use of LAMICTAL as monotherapy (100 to 400 mg/day) in adult patients (≥18 years of age) with Bipolar Disorder in the 2 double-blind, placebo-controlled trials of 18 months’ duration, and numerically more frequent than in placebo-treated patients are included in Table 12. Adverse reactions that occurred in at least 5% of patients and were numerically more common during the dose-escalation phase of LAMICTAL in these trials (when patients may have been receiving concomitant medications) compared with the monotherapy phase were: headache (25%), rash (11%), dizziness (10%), diarrhea (8%), dream abnormality (6%), and pruritus (6%).

During the monotherapy phase of the double-blind, placebo-controlled trials of 18 months’ duration, 13% of 227 patients who received LAMICTAL (100 to 400 mg/day), 16% of 190 patients who received placebo, and 23% of 166 patients who received lithium discontinued therapy because of an adverse reaction. The adverse reactions which most commonly led to discontinuation of LAMICTAL were rash (3%) and mania/hypomania/mixed mood adverse reactions (2%). Approximately 16% of 2,401 patients who received LAMICTAL (50 to 500 mg/day) for Bipolar Disorder in premarketing trials discontinued therapy because of an adverse reaction, most commonly due to rash (5%) and mania/hypomania/mixed mood adverse reactions (2%).

The overall adverse reaction profile for LAMICTAL was similar between females and males, between elderly and nonelderly patients, and among racial groups.

Table 12. Treatment-Emergent Adverse Reaction Incidence in 2 Placebo-Controlled Trials in Adults With Bipolar I Disordera (Adverse reactions in at least 5% of patients treated with LAMICTAL as monotherapy and numerically more frequent than in the placebo group.)
Body System/; Adverse Reaction | Percent of Patients Receiving LAMICTAL; (n = 227) | Percent of Patients Receiving Placebo; (n = 190)
General
Back pain | 8 | 6
Fatigue | 8 | 5
Abdominal pain | 6 | 3
Digestive
Nausea | 14 | 11
Constipation | 5 | 2
Vomiting | 5 | 2
Nervous System
Insomnia | 10 | 6
Somnolence | 9 | 7
Xerostomia (dry mouth) | 6 | 4
Respiratory
Rhinitis | 7 | 4
Exacerbation of cough | 5 | 3
Pharyngitis | 5 | 4
Skin
Rash (nonserious)b | 7 | 5

aPatients in these studies were converted to LAMICTAL (100 to 400 mg/day) or placebo monotherapy from add-on therapy with other psychotropic medications. Patients may have reported multiple adverse reactions during the study; thus, patients may be included in more than one category.

bIn the overall bipolar and other mood disorders clinical trials, the rate of serious rash was 0.08% (1 of 1,233) of adult patients who received LAMICTAL as initial monotherapy and 0.13% (2 of 1,538) of adult patients who received LAMICTAL as adjunctive therapy [see Warnings and Precautions (5.1)].

These adverse reactions were usually mild to moderate in intensity. Other reactions that occurred in 5% or more patients but equally or more frequently in the placebo group included: dizziness, mania, headache, infection, influenza, pain, accidental injury, diarrhea, and dyspepsia.

Adverse reactions that occurred with a frequency of less than 5% and greater than 1% of patients receiving LAMICTAL and numerically more frequent than placebo were:

General: Fever, neck pain.

Cardiovascular: Migraine.

Digestive: Flatulence.

Metabolic and Nutritional: Weight gain, edema.

Musculoskeletal: Arthralgia, myalgia.

Nervous System: Amnesia, depression, agitation, emotional lability, dyspraxia, abnormal thoughts, dream abnormality, hypoesthesia.

Respiratory: Sinusitis.

Urogenital: Urinary frequency.

Adverse Reactions Following Abrupt Discontinuation: In the 2 maintenance trials, there was no increase in the incidence, severity, or type of adverse reactions in Bipolar Disorder patients after abruptly terminating therapy with LAMICTAL. In clinical trials in patients with Bipolar Disorder, 2 patients experienced seizures shortly after abrupt withdrawal of LAMICTAL. However, there were confounding factors that may have contributed to the occurrence of seizures in these bipolar patients [see Warnings and Precautions (5.9)].

Mania/Hypomania/Mixed Episodes: During the double-blind, placebo-controlled clinical trials in Bipolar I Disorder in which patients were converted to monotherapy with LAMICTAL (100 to 400 mg/day) from other psychotropic medications and followed for up to 18 months, the rates of manic or hypomanic or mixed mood episodes reported as adverse reactions were 5% for patients treated with LAMICTAL (n = 227), 4% for patients treated with lithium (n = 166), and 7% for patients treated with placebo (n = 190). In all bipolar controlled trials combined, adverse reactions of mania (including hypomania and mixed mood episodes) were reported in 5% of patients treated with LAMICTAL (n = 956), 3% of patients treated with lithium (n = 280), and 4% of patients treated with placebo (n = 803).

6.2 Other Adverse Reactions Observed in All Clinical Trials

LAMICTAL has been administered to 6,694 individuals for whom complete adverse reaction data was captured during all clinical trials, only some of which were placebo controlled. During these trials, all adverse reactions were recorded by the clinical investigators using terminology of their own choosing. To provide a meaningful estimate of the proportion of individuals having adverse reactions, similar types of adverse reactions were grouped into a smaller number of standardized categories using modified COSTART dictionary terminology. The frequencies presented represent the proportion of the 6,694 individuals exposed to LAMICTAL who experienced an event of the type cited on at least one occasion while receiving LAMICTAL. All reported adverse reactions are included except those already listed in the previous tables or elsewhere in the labeling, those too general to be informative, and those not reasonably associated with the use of the drug.

Adverse reactions are further classified within body system categories and enumerated in order of decreasing frequency using the following definitions: frequent adverse reactions are defined as those occurring in at least 1/100 patients; infrequent adverse reactions are those occurring in 1/100 to 1/1,000 patients; rare adverse reactions are those occurring in fewer than 1/1,000 patients.

Body as a Whole: Infrequent: Allergic reaction, chills, and malaise.

Cardiovascular System: Infrequent: Flushing, hot flashes, hypertension, palpitations, postural hypotension, syncope, tachycardia, and vasodilation.

Dermatological: Infrequent: Acne, alopecia, hirsutism, maculopapular rash, skin discoloration, and urticaria. Rare: Angioedema, erythema, exfoliative dermatitis, fungal dermatitis, herpes zoster, leukoderma, multiforme erythema, petechial rash, pustular rash, Stevens-Johnson syndrome, and vesiculobullous rash.

Digestive System: Infrequent: Dysphagia, eructation, gastritis, gingivitis, increased appetite, increased salivation, liver function tests abnormal, and mouth ulceration. Rare: Gastrointestinal hemorrhage, glossitis, gum hemorrhage, gum hyperplasia, hematemesis, hemorrhagic colitis, hepatitis, melena, stomach ulcer, stomatitis, and tongue edema.

Endocrine System: Rare: Goiter and hypothyroidism.

Hematologic and Lymphatic System: Infrequent: Ecchymosis and leukopenia. Rare: Anemia, eosinophilia, fibrin decrease, fibrinogen decrease, iron deficiency anemia, leukocytosis, lymphocytosis, macrocytic anemia, petechia, and thrombocytopenia.

Metabolic and Nutritional Disorders: Infrequent: Aspartate transaminase increased. Rare: Alcohol intolerance, alkaline phosphatase increase, alanine transaminase increase, bilirubinemia, general edema, gamma glutamyl transpeptidase increase, and hyperglycemia.

Musculoskeletal System: Infrequent: Arthritis, leg cramps, myasthenia, and twitching. Rare: Bursitis, muscle atrophy, pathological fracture, and tendinous contracture.

Nervous System: Frequent: Confusion and paresthesia. Infrequent: Akathisia, apathy, aphasia, central nervous system (CNS) depression, depersonalization, dysarthria, dyskinesia, euphoria, hallucinations, hostility, hyperkinesia, hypertonia, libido decreased, memory decrease, mind racing, movement disorder, myoclonus, panic attack, paranoid reaction, personality disorder, psychosis, sleep disorder, stupor, and suicidal ideation. Rare: Choreoathetosis, delirium, delusions, dysphoria, dystonia, extrapyramidal syndrome, faintness, grand mal convulsions, hemiplegia, hyperalgesia, hyperesthesia, hypokinesia, hypotonia, manic depression reaction, muscle spasm, neuralgia, neurosis, paralysis, and peripheral neuritis.

Respiratory System: Infrequent: Yawn. Rare: Hiccup and hyperventilation.

Special Senses: Frequent: Amblyopia. Infrequent: Abnormality of accommodation, conjunctivitis, dry eyes, ear pain, photophobia, taste perversion, and tinnitus. Rare: Deafness, lacrimation disorder, oscillopsia, parosmia, ptosis, strabismus, taste loss, uveitis, and visual field defect.

Urogenital System: Infrequent: Abnormal ejaculation, hematuria, impotence, menorrhagia, polyuria, and urinary incontinence. Rare: Acute kidney failure, anorgasmia, breast abscess, breast neoplasm, creatinine increase, cystitis, dysuria, epididymitis, female lactation, kidney failure, kidney pain, nocturia, urinary retention, and urinary urgency.

6.3 Postmarketing Experience

The following adverse events (not listed above in clinical trials or other sections of the prescribing information) have been identified during postapproval use of LAMICTAL. Because these events are reported voluntarily from a population of uncertain size, it is not always possible to reliably estimate their frequency or establish a causal relationship to drug exposure.

Blood and Lymphatic: Agranulocytosis, hemolytic anemia, lymphadenopathy not associated with hypersensitivity disorder.

Gastrointestinal: Esophagitis.

Hepatobiliary Tract and Pancreas: Pancreatitis.

Immunologic: Lupus-like reaction, vasculitis.

Lower Respiratory: Apnea.

Musculoskeletal: Rhabdomyolysis has been observed in patients experiencing hypersensitivity reactions.

Neurology: Exacerbation of Parkinsonian symptoms in patients with pre-existing Parkinson’s disease, tics.

Non-site Specific: Progressive immunosuppression.

7 DRUG INTERACTIONS

Significant drug interactions with lamotrigine are summarized in Table 13. Additional details of these drug interaction studies are provided in the Clinical Pharmacology section [see Clinical Pharmacology (12.3)].

Table 13. Established and Other Potentially Significant Drug Interactions
Concomitant Drug | Effect on Concentration of Lamotrigine or Concomitant Drug | Clinical Comment
Estrogen-containing oral contraceptive preparations containing 30 mcg ethinylestradiol and 150 mcg levonorgestrel | ↓ lamotrigine | Decreased lamotrigine levels approximately 50%.
 | ↓ levonorgestrel | Decrease in levonorgestrel component by 19%.
Carbamazepine (CBZ) and CBZ epoxide | ↓ lamotrigine | Addition of carbamazepine decreases lamotrigine concentration approximately 40%.
 | ? CBZ epoxide | May increase CBZ epoxide levels
Phenobarbital/Primidone | ↓ lamotrigine | Decreased lamotrigine concentration approximately 40%.
Phenytoin (PHT) | ↓ lamotrigine | Decreased lamotrigine concentration approximately 40%.
Rifampin | ↓ lamotrigine | Decreased lamotrigine AUC approximately 40%.
Valproate | ↑ lamotrigine | Increased lamotrigine concentrations slightly more than 2-fold.
 | ? valproate | Decreased valproate concentrations an average of 25% over a 3-week period then stabilized in healthy volunteers; no change in controlled clinical trials in epilepsy patients.

↓= Decreased (induces lamotrigine glucuronidation).

↑= Increased (inhibits lamotrigine glucuronidation).

? = Conflicting data.

8 USE IN SPECIFIC POPULATIONS

8.1 Pregnancy

Teratogenic Effects: Pregnancy Category C. No evidence of teratogenicity was found in mice, rats, or rabbits when lamotrigine was orally administered to pregnant animals during the period of organogenesis at doses up to 1.2, 0.5, and 1.1 times, respectively, on a mg/m^2 basis, the highest usual human maintenance dose (i.e., 500 mg/day). However, maternal toxicity and secondary fetal toxicity producing reduced fetal weight and/or delayed ossification were seen in mice and rats, but not in rabbits at these doses. Teratology studies were also conducted using bolus intravenous administration of the isethionate salt of lamotrigine in rats and rabbits. In rat dams administered an intravenous dose at 0.6 times the highest usual human maintenance dose, the incidence of intrauterine death without signs of teratogenicity was increased.

A behavioral teratology study was conducted in rats dosed during the period of organogenesis. At day 21 postpartum, offspring of dams receiving 5 mg/kg/day or higher displayed a significantly longer latent period for open field exploration and a lower frequency of rearing. In a swimming maze test performed on days 39 to 44 postpartum, time to completion was increased in offspring of dams receiving 25 mg/kg/day. These doses represent 0.1 and 0.5 times the clinical dose on a mg/m^2 basis, respectively.

Lamotrigine did not affect fertility, teratogenesis, or postnatal development when rats were dosed prior to and during mating, and throughout gestation and lactation at doses equivalent to 0.4 times the highest usual human maintenance dose on a mg/m^2 basis.

When pregnant rats were orally dosed at 0.1, 0.14, or 0.3 times the highest human maintenance dose (on a mg/m^2 basis) during the latter part of gestation (days 15 to 20), maternal toxicity and fetal death were seen. In dams, food consumption and weight gain were reduced, and the gestation period was slightly prolonged (22.6 vs. 22.0 days in the control group). Stillborn pups were found in all 3 drug-treated groups with the highest number in the high-dose group. Postnatal death was also seen, but only in the 2 highest doses, and occurred between days 1 and 20. Some of these deaths appear to be drug-related and not secondary to the maternal toxicity. A no-observed-effect level (NOEL) could not be determined for this study.

Although lamotrigine was not found to be teratogenic in the above studies, lamotrigine decreases fetal folate concentrations in rats, an effect known to be associated with teratogenesis in animals and humans. There are no adequate and well-controlled studies in pregnant women. Because animal reproduction studies are not always predictive of human response, this drug should be used during pregnancy only if the potential benefit justifies the potential risk to the fetus.

Non-Teratogenic Effects: As with other AEDs, physiological changes during pregnancy may affect lamotrigine concentrations and/or therapeutic effect. There have been reports of decreased lamotrigine concentrations during pregnancy and restoration of pre-partum concentrations after delivery. Dosage adjustments may be necessary to maintain clinical response.

Pregnancy Exposure Registry: To provide information regarding the effects of in utero exposure to LAMICTAL, physicians are advised to recommend that pregnant patients taking LAMICTAL enroll in the North American Antiepileptic Drug (NAAED) Pregnancy Registry. This can be done by calling the toll-free number 1-888-233-2334, and must be done by patients themselves. Information on the registry can also be found at the website http://www.aedpregnancyregistry.org/.

Physicians are also encouraged to register patients in the Lamotrigine Pregnancy Registry; enrollment in this registry must be done prior to any prenatal diagnostic tests and before fetal outcome is known. Physicians can obtain information by calling the Lamotrigine Pregnancy Registry at 1-800-336-2176 (toll-free).

8.2 Labor and Delivery

The effect of LAMICTAL on labor and delivery in humans is unknown.

8.3 Nursing Mothers

Lamotrigine is present in milk from lactating women taking LAMICTAL. Data from multiple small studies indicate that lamotrigine plasma levels in human milk-fed infants have been reported to be as high as 50% of the maternal serum levels. Neonates and young infants are at risk for high serum levels because maternal serum and milk levels can rise to high levels postpartum if lamotrigine dosage has been increased during pregnancy but not later reduced to the pre-pregnancy dosage. Lamotrigine exposure is further increased due to the immaturity of the infant glucuronidation capacity needed for drug clearance. Events including apnea, drowsiness, and poor sucking have been reported in infants who have been human milk-fed by mothers using lamotrigine; whether or not these events were caused by lamotrigine is unknown. Human milk-fed infants should be closely monitored for adverse events resulting from lamotrigine. Measurement of infant serum levels should be performed to rule out toxicity if concerns arise. Human milk-feeding should be discontinued in infants with lamotrigine toxicity. Caution should be exercised when LAMICTAL is administered to a nursing woman.

8.4 Pediatric Use

LAMICTAL is indicated for adjunctive therapy in patients ≥2 years of age for partial seizures, the generalized seizures of Lennox-Gastaut syndrome, and primary generalized tonic-clonic seizures.

Safety and efficacy of LAMICTAL, used as adjunctive treatment for partial seizures, were not demonstrated in a small randomized, double-blind, placebo-controlled, withdrawal study in very young pediatric patients (1 to 24 months of age). LAMICTAL was associated with an increased risk for infectious adverse reactions (LAMICTAL 37%, placebo 5%), and respiratory adverse reactions (LAMICTAL 26%, placebo 5%). Infectious adverse reactions included bronchiolitis, bronchitis, ear infection, eye infection, otitis externa, pharyngitis, urinary tract infection, and viral infection. Respiratory adverse reactions included nasal congestion, cough, and apnea.

Safety and effectiveness in patients below the age of 18 years with Bipolar Disorder have not been established.

8.5 Geriatric Use

Clinical studies of LAMICTAL for epilepsy and in Bipolar Disorder did not include sufficient numbers of subjects 65 years of age and over to determine whether they respond differently from younger subjects or exhibit a different safety profile than that of younger patients. In general, dose selection for an elderly patient should be cautious, usually starting at the low end of the dosing range, reflecting the greater frequency of decreased hepatic, renal, or cardiac function, and of concomitant disease or other drug therapy.

8.6 Patients With Hepatic Impairment

Experience in patients with hepatic impairment is limited. Based on a clinical pharmacology study in 24 patients with mild, moderate, and severe liver impairment [see Clinical Pharmacology (12.3)], the following general recommendations can be made. No dosage adjustment is needed in patients with mild liver impairment. Initial, escalation, and maintenance doses should generally be reduced by approximately 25% in patients with moderate and severe liver impairment without ascites and 50% in patients with severe liver impairment with ascites. Escalation and maintenance doses may be adjusted according to clinical response [see Dosage and Administration (2.1)].

8.7 Patients With Renal Impairment

Lamotrigine is metabolized mainly by glucuronic acid conjugation, with the majority of the metabolites being recovered in the urine. In a small study comparing a single dose of lamotrigine in patients with varying degrees of renal impairment with healthy volunteers, the plasma half-life of lamotrigine was significantly longer in the patients with renal impairment [see Clinical Pharmacology (12.3)].

Initial doses of LAMICTAL should be based on patients’ AED regimens; reduced maintenance doses may be effective for patients with significant renal impairment. Few patients with severe renal impairment have been evaluated during chronic treatment with LAMICTAL. Because there is inadequate experience in this population, LAMICTAL should be used with caution in these patients [see Dosage and Administration (2.1)].

10 OVERDOSAGE

10.1 Human Overdose Experience

Overdoses involving quantities up to 15 g have been reported for LAMICTAL, some of which have been fatal. Overdose has resulted in ataxia, nystagmus, increased seizures, decreased level of consciousness, coma, and intraventricular conduction delay.

10.2 Management of Overdose

There are no specific antidotes for lamotrigine. Following a suspected overdose, hospitalization of the patient is advised. General supportive care is indicated, including frequent monitoring of vital signs and close observation of the patient. If indicated, emesis should be induced; usual precautions should be taken to protect the airway. It should be kept in mind that lamotrigine is rapidly absorbed [see Clinical Pharmacology (12.3)]. It is uncertain whether hemodialysis is an effective means of removing lamotrigine from the blood. In 6 renal failure patients, about 20% of the amount of lamotrigine in the body was removed by hemodialysis during a 4-hour session. A Poison Control Center should be contacted for information on the management of overdosage of LAMICTAL.

11 DESCRIPTION

LAMICTAL (lamotrigine), an AED of the phenyltriazine class, is chemically unrelated to existing AEDs. Its chemical name is 3,5-diamino-6-(2,3-dichlorophenyl)-as-triazine, its molecular formula is C9H7N5Cl2, and its molecular weight is 256.09. Lamotrigine is a white to pale cream-colored powder and has a pKa of 5.7. Lamotrigine is very slightly soluble in water (0.17 mg/mL at 25°C) and slightly soluble in 0.1 M HCl (4.1 mg/mL at 25°C). The structural formula is:

LAMICTAL Tablets are supplied for oral administration as 25 mg (white), 100 mg (peach), 150 mg (cream), and 200 mg (blue) tablets. Each tablet contains the labeled amount of lamotrigine and the following inactive ingredients: lactose; magnesium stearate; microcrystalline cellulose; povidone; sodium starch glycolate; FD&C Yellow No. 6 Lake (100-mg tablet only); ferric oxide, yellow (150-mg tablet only); and FD&C Blue No. 2 Lake (200-mg tablet only).

LAMICTAL Chewable Dispersible Tablets are supplied for oral administration. The tablets contain 2 mg (white), 5 mg (white), or 25 mg (white) of lamotrigine and the following inactive ingredients: blackcurrant flavor, calcium carbonate, low-substituted hydroxypropylcellulose, magnesium aluminum silicate, magnesium stearate, povidone, saccharin sodium, and sodium starch glycolate.

LAMICTAL ODT Orally Disintegrating Tablets are supplied for oral administration. The tablets contain 25 mg (white to off-white), 50 mg (white to off-white), 100 mg (white to off-white), or 200 mg (white to off-white) of lamotrigine and the following inactive ingredients: artificial cherry flavor, crospovidone, ethylcellulose, magnesium stearate, mannitol, polyethylene, and sucralose.

LAMICTAL ODT Orally Disintegrating Tablets are formulated using technologies (Microcaps® and AdvaTab®) designed to mask the bitter taste of lamotrigine and achieve a rapid dissolution profile. Tablet characteristics including flavor, mouth-feel, after-taste, and ease of use were rated as favorable in a study of 108 healthy volunteers.

12 CLINICAL PHARMACOLOGY

12.1 Mechanism of Action

The precise mechanism(s) by which lamotrigine exerts its anticonvulsant action are unknown. In animal models designed to detect anticonvulsant activity, lamotrigine was effective in preventing seizure spread in the maximum electroshock (MES) and pentylenetetrazol (scMet) tests, and prevented seizures in the visually and electrically evoked after-discharge (EEAD) tests for antiepileptic activity. Lamotrigine also displayed inhibitory properties in the kindling model in rats both during kindling development and in the fully kindled state. The relevance of these models to human epilepsy, however, is not known.

One proposed mechanism of action of lamotrigine, the relevance of which remains to be established in humans, involves an effect on sodium channels. In vitro pharmacological studies suggest that lamotrigine inhibits voltage-sensitive sodium channels, thereby stabilizing neuronal membranes and consequently modulating presynaptic transmitter release of excitatory amino acids (e.g., glutamate and aspartate).

Although the relevance for human use is unknown, the following data characterize the performance of lamotrigine in receptor binding assays. Lamotrigine had a weak inhibitory effect on the serotonin 5-HT3 receptor (IC50 = 18 µM). It does not exhibit high affinity binding (IC50>100 µM) to the following neurotransmitter receptors: adenosine A1 and A2; adrenergic α1, α2, and β; dopamine D1 and D2; γ-aminobutyric acid (GABA) A and B; histamine H1; kappa opioid; muscarinic acetylcholine; and serotonin 5-HT2. Studies have failed to detect an effect of lamotrigine on dihydropyridine-sensitive calcium channels. It had weak effects at sigma opioid receptors (IC50 = 145 µM). Lamotrigine did not inhibit the uptake of norepinephrine, dopamine, or serotonin (IC50>200 µM) when tested in rat synaptosomes and/or human platelets in vitro.

Effect of Lamotrigine on N-Methyl d-Aspartate-Receptor Mediated Activity: Lamotrigine did not inhibit N-methyl d-aspartate (NMDA)-induced depolarizations in rat cortical slices or NMDA-induced cyclic GMP formation in immature rat cerebellum, nor did lamotrigine displace compounds that are either competitive or noncompetitive ligands at this glutamate receptor complex (CNQX, CGS, TCHP). The IC50 for lamotrigine effects on NMDA-induced currents (in the presence of 3 µM of glycine) in cultured hippocampal neurons exceeded 100 µM.

The mechanisms by which lamotrigine exerts its therapeutic action in Bipolar Disorder have not been established.

12.2 Pharmacodynamics

Folate Metabolism: In vitro, lamotrigine inhibited dihydrofolate reductase, the enzyme that catalyzes the reduction of dihydrofolate to tetrahydrofolate. Inhibition of this enzyme may interfere with the biosynthesis of nucleic acids and proteins. When oral daily doses of lamotrigine were given to pregnant rats during organogenesis, fetal, placental, and maternal folate concentrations were reduced. Significantly reduced concentrations of folate are associated with teratogenesis [see Use in Specific Populations (8.1)]. Folate concentrations were also reduced in male rats given repeated oral doses of lamotrigine. Reduced concentrations were partially returned to normal when supplemented with folinic acid.

Accumulation in Kidneys: Lamotrigine accumulated in the kidney of the male rat, causing chronic progressive nephrosis, necrosis, and mineralization. These findings are attributed to α-2 microglobulin, a species- and sex-specific protein that has not been detected in humans or other animal species.

Melanin Binding: Lamotrigine binds to melanin-containing tissues, e.g., in the eye and pigmented skin. It has been found in the uveal tract up to 52 weeks after a single dose in rodents.

Cardiovascular: In dogs, lamotrigine is extensively metabolized to a 2-N-methyl metabolite. This metabolite causes dose-dependent prolongations of the PR interval, widening of the QRS complex, and, at higher doses, complete AV conduction block. Similar cardiovascular effects are not anticipated in humans because only trace amounts of the 2-N-methyl metabolite (<0.6% of lamotrigine dose) have been found in human urine [see Clinical Pharmacology (12.3)]. However, it is conceivable that plasma concentrations of this metabolite could be increased in patients with a reduced capacity to glucuronidate lamotrigine (e.g., in patients with liver disease).

12.3 Pharmacokinetics

The pharmacokinetics of lamotrigine have been studied in patients with epilepsy, healthy young and elderly volunteers, and volunteers with chronic renal failure. Lamotrigine pharmacokinetic parameters for adult and pediatric patients and healthy normal volunteers are summarized in Tables 14 and 16.

Table 14. Meana Pharmacokinetic Parameters in Healthy Volunteers and Adult Patients With Epilepsy
Adult Study Population | Number of Subjects | Tmax: Time of Maximum Plasma Concentration; (hr) | t½:; Elimination Half-life; (hr) | Cl/F:; Apparent Plasma Clearance (mL/min/kg)
Healthy volunteers taking no other medications:
Single-dose LAMICTAL | 179 | 2.2; (0.25-12.0) | 32.8; (14.0-103.0) | 0.44; (0.12-1.10)
Multiple-dose LAMICTAL | 36 | 1.7; (0.5-4.0) | 25.4; (11.6-61.6) | 0.58; (0.24-1.15)
Healthy volunteers taking valproate:
Single-dose LAMICTAL | 6 | 1.8; (1.0-4.0) | 48.3; (31.5-88.6) | 0.30; (0.14-0.42)
Multiple-dose LAMICTAL | 18 | 1.9; (0.5-3.5) | 70.3; (41.9-113.5) | 0.18; (0.12-0.33)
Patients with epilepsy taking valproate only:
Single-dose LAMICTAL | 4 | 4.8; (1.8-8.4) | 58.8; (30.5-88.8) | 0.28; (0.16-0.40)
Patients with epilepsy taking carbamazepine, phenytoin, phenobarbital, or primidoneb plus valproate:
Single-dose LAMICTAL | 25 | 3.8; (1.0-10.0) | 27.2; (11.2-51.6) | 0.53; (0.27-1.04)
Patients with epilepsy taking carbamazepine, phenytoin, phenobarbital, or primidone:b
Single-dose LAMICTAL | 24 | 2.3; (0.5-5.0) | 14.4; (6.4-30.4) | 1.10; (0.51-2.22)
Multiple-dose LAMICTAL | 17 | 2.0; (0.75-5.93) | 12.6; (7.5-23.1) | 1.21; (0.66-1.82)

aThe majority of parameter means determined in each study had coefficients of variation between 20% and 40% for half-life and Cl/F and between 30% and 70% for Tmax. The overall mean values were calculated from individual study means that were weighted based on the number of volunteers/patients in each study. The numbers in parentheses below each parameter mean represent the range of individual volunteer/patient values across studies.

bCarbamazepine, phenobarbital, phenytoin, and primidone have been shown to increase the apparent clearance of lamotrigine. Estrogen-containing oral contraceptives and other drugs such as rifampin that induce lamotrigine glucuronidation have also been shown to increase the apparent clearance of lamotrigine [see Drug Interactions (7)].

Absorption: Lamotrigine is rapidly and completely absorbed after oral administration with negligible first-pass metabolism (absolute bioavailability is 98%). The bioavailability is not affected by food. Peak plasma concentrations occur anywhere from 1.4 to 4.8 hours following drug administration. The lamotrigine chewable/dispersible tablets were found to be equivalent, whether they were administered as dispersed in water, chewed and swallowed, or swallowed as whole, to the lamotrigine compressed tablets in terms of rate and extent of absorption. In terms of rate and extent of absorption, lamotrigine orally disintegrating tablets whether disintegrated in the mouth or swallowed whole with water were equivalent to the lamotrigine compressed tablets swallowed with water.

Dose Proportionality: In healthy volunteers not receiving any other medications and given single doses, the plasma concentrations of lamotrigine increased in direct proportion to the dose administered over the range of 50 to 400 mg. In 2 small studies (n = 7 and 8) of patients with epilepsy who were maintained on other AEDs, there also was a linear relationship between dose and lamotrigine plasma concentrations at steady state following doses of 50 to 350 mg twice daily.

Distribution: Estimates of the mean apparent volume of distribution (Vd/F) of lamotrigine following oral administration ranged from 0.9 to 1.3 L/kg. Vd/F is independent of dose and is similar following single and multiple doses in both patients with epilepsy and in healthy volunteers.

Protein Binding: Data from in vitro studies indicate that lamotrigine is approximately 55% bound to human plasma proteins at plasma lamotrigine concentrations from 1 to 10 mcg/mL (10 mcg/mL is 4 to 6 times the trough plasma concentration observed in the controlled efficacy trials). Because lamotrigine is not highly bound to plasma proteins, clinically significant interactions with other drugs through competition for protein binding sites are unlikely. The binding of lamotrigine to plasma proteins did not change in the presence of therapeutic concentrations of phenytoin, phenobarbital, or valproate. Lamotrigine did not displace other AEDs (carbamazepine, phenytoin, phenobarbital) from protein-binding sites.

Metabolism: Lamotrigine is metabolized predominantly by glucuronic acid conjugation; the major metabolite is an inactive 2-N-glucuronide conjugate. After oral administration of 240 mg of ^14C-lamotrigine (15 μCi) to 6 healthy volunteers, 94% was recovered in the urine and 2% was recovered in the feces. The radioactivity in the urine consisted of unchanged lamotrigine (10%), the 2-N-glucuronide (76%), a 5-N-glucuronide (10%), a 2-N-methyl metabolite (0.14%), and other unidentified minor metabolites (4%).

Enzyme Induction: The effects of lamotrigine on the induction of specific families of mixed-function oxidase isozymes have not been systematically evaluated.

Following multiple administrations (150 mg twice daily) to normal volunteers taking no other medications, lamotrigine induced its own metabolism, resulting in a 25% decrease in t½ and a 37% increase in Cl/F at steady state compared with values obtained in the same volunteers following a single dose. Evidence gathered from other sources suggests that self-induction by lamotrigine may not occur when lamotrigine is given as adjunctive therapy in patients receiving enzyme-inducing drugs such as carbamazepine, phenytoin, phenobarbital, primidone, or drugs such as rifampin that induce lamotrigine glucuronidation [see Drug Interactions (7)].

Elimination: The elimination half-life and apparent clearance of lamotrigine following administration of LAMICTAL to adult patients with epilepsy and healthy volunteers is summarized in Table 14. Half-life and apparent oral clearance vary depending on concomitant AEDs.

Drug Interactions: The apparent clearance of lamotrigine is affected by the coadministration of certain medications [see Warnings and Precautions (5.8, 5.12), Drug Interactions (7)].

The net effects of drug interactions with LAMICTAL are summarized in Tables 13 and 15, followed by details of the drug interaction studies below.

Table 15. Summary of Drug Interactions With LAMICTAL
Drug | Drug Plasma Concentration With Adjunctive LAMICTALa | Lamotrigine Plasma Concentration With Adjunctive Drugsb
Oral contraceptives (e.g., ethinylestradiol/levonorgestrel)c | ↔d | ↓
Bupropion | Not assessed | ↔
Carbamazepine (CBZ) | ↔ | ↓
CBZ epoxidee | ?
Felbamate | Not assessed | ↔
Gabapentin | Not assessed | ↔
Levetiracetam | ↔ | ↔
Lithium | ↔ | Not assessed
Olanzapine | ↔ | ↔f
Oxcarbazepine | ↔ | ↔
10-monohydroxy oxcarbazepine metaboliteg | ↔
Phenobarbital/primidone | ↔ | ↓
Phenytoin (PHT) | ↔ | ↓
Pregabalin | ↔ | ↔
Rifampin | Not assessed | ↓
Topiramate | ↔h | ↔
Valproate | ↓ | ↑
Valproate + PHT and/or CBZ | Not assessed | ↔
Zonisamide | Not assessed | ↔

aFrom adjunctive clinical trials and volunteer studies.

bNet effects were estimated by comparing the mean clearance values obtained in adjunctive clinical trials and volunteer studies.

cThe effect of other hormonal contraceptive preparations or hormone replacement therapy on the pharmacokinetics of lamotrigine has not been systematically evaluated in clinical trials, although the effect may be similar to that seen with the ethinylestradiol/levonorgestrel combinations.

dModest decrease in levonorgestrel.

eNot administered, but an active metabolite of carbamazepine.

fSlight decrease, not expected to be clinically relevant.

gNot administered, but an active metabolite of oxcarbazepine.

hSlight increase, not expected to be clinically relevant.

↔ = No significant effect.

? = Conflicting data.

Estrogen-Containing Oral Contraceptives: In 16 female volunteers, an oral contraceptive preparation containing 30 mcg ethinylestradiol and 150 mcg levonorgestrel increased the apparent clearance of lamotrigine (300 mg/day) by approximately 2-fold with mean decreases in AUC of 52% and in Cmax of 39%. In this study, trough serum lamotrigine concentrations gradually increased and were approximately 2-fold higher on average at the end of the week of the inactive hormone preparation compared with trough lamotrigine concentrations at the end of the active hormone cycle.

Gradual transient increases in lamotrigine plasma levels (approximate 2-fold increase) occurred during the week of inactive hormone preparation (“pill-free” week) for women not also taking a drug that increased the clearance of lamotrigine (carbamazepine, phenytoin, phenobarbital, primidone, or other drugs such as rifampin that induce lamotrigine glucuronidation [see Drug Interactions (7)]). The increase in lamotrigine plasma levels will be greater if the dose of LAMICTAL is increased in the few days before or during the “pill-free”week. Increases in lamotrigine plasma levels could result in dose-dependent adverse reactions.

In the same study, coadministration of LAMICTAL (300 mg/day) in 16 female volunteers did not affect the pharmacokinetics of the ethinylestradiol component of the oral contraceptive preparation. There were mean decreases in the AUC and Cmax of the levonorgestrel component of 19% and 12%, respectively. Measurement of serum progesterone indicated that there was no hormonal evidence of ovulation in any of the 16 volunteers, although measurement of serum FSH, LH, and estradiol indicated that there was some loss of suppression of the hypothalamic-pituitary-ovarian axis.

The effects of doses of LAMICTAL other than 300 mg/day have not been systematically evaluated in controlled clinical trials.

The clinical significance of the observed hormonal changes on ovulatory activity is unknown. However, the possibility of decreased contraceptive efficacy in some patients cannot be excluded. Therefore, patients should be instructed to promptly report changes in their menstrual pattern (e.g., break-through bleeding).

Dosage adjustments may be necessary for women receiving estrogen-containing oral contraceptive preparations [see Dosage and Administration (2.1)].

Other Hormonal Contraceptives or Hormone Replacement Therapy: The effect of other hormonal contraceptive preparations or hormone replacement therapy on the pharmacokinetics of lamotrigine has not been systematically evaluated. It has been reported that ethinylestradiol, not progestogens, increased the clearance of lamotrigine up to 2-fold, and the progestin-only pills had no effect on lamotrigine plasma levels. Therefore, adjustments to the dosage of LAMICTAL in the presence of progestogens alone will likely not be needed.

Bupropion: The pharmacokinetics of a 100-mg single dose of LAMICTAL in healthy volunteers (n = 12) were not changed by coadministration of bupropion sustained-release formulation (150 mg twice daily) starting 11 days before LAMICTAL.

Carbamazepine: LAMICTAL has no appreciable effect on steady-state carbamazepine plasma concentration. Limited clinical data suggest there is a higher incidence of dizziness, diplopia, ataxia, and blurred vision in patients receiving carbamazepine with lamotrigine than in patients receiving other AEDs with lamotrigine [see Adverse Reactions (6.1)]. The mechanism of this interaction is unclear. The effect of lamotrigine on plasma concentrations of carbamazepine-epoxide is unclear. In a small subset of patients (n = 7) studied in a placebo-controlled trial, lamotrigine had no effect on carbamazepine-epoxide plasma concentrations, but in a small, uncontrolled study (n = 9), carbamazepine-epoxide levels increased.

The addition of carbamazepine decreases lamotrigine steady-state concentrations by approximately 40%.

Felbamate: In a study of 21 healthy volunteers, coadministration of felbamate (1,200 mg twice daily) with lamotrigine (100 mg twice daily for 10 days) appeared to have no clinically relevant effects on the pharmacokinetics of lamotrigine.

Folate Inhibitors: Lamotrigine is a weak inhibitor of dihydrofolate reductase. Prescribers should be aware of this action when prescribing other medications that inhibit folate metabolism.

Gabapentin: Based on a retrospective analysis of plasma levels in 34 patients who received lamotrigine both with and without gabapentin, gabapentin does not appear to change the apparent clearance of lamotrigine.

Levetiracetam: Potential drug interactions between levetiracetam and lamotrigine were assessed by evaluating serum concentrations of both agents during placebo-controlled clinical trials. These data indicate that lamotrigine does not influence the pharmacokinetics of levetiracetam and that levetiracetam does not influence the pharmacokinetics of lamotrigine.

Lithium: The pharmacokinetics of lithium were not altered in healthy subjects (n = 20) by coadministration of lamotrigine (100 mg/day) for 6 days.

Olanzapine: The AUC and Cmax of olanzapine were similar following the addition of olanzapine (15 mg once daily) to lamotrigine (200 mg once daily) in healthy male volunteers (n = 16) compared with the AUC and Cmax in healthy male volunteers receiving olanzapine alone (n = 16).

In the same study, the AUC and Cmax of lamotrigine were reduced on average by 24% and 20%, respectively, following the addition of olanzapine to lamotrigine in healthy male volunteers compared with those receiving lamotrigine alone. This reduction in lamotrigine plasma concentrations is not expected to be clinically relevant.

Oxcarbazepine: The AUC and Cmax of oxcarbazepine and its active 10-monohydroxy oxcarbazepine metabolite were not significantly different following the addition of oxcarbazepine (600 mg twice daily) to lamotrigine (200 mg once daily) in healthy male volunteers (n = 13) compared with healthy male volunteers receiving oxcarbazepine alone (n = 13).

In the same study, the AUC and Cmax of lamotrigine were similar following the addition of oxcarbazepine (600 mg twice daily) to LAMICTAL in healthy male volunteers compared with those receiving LAMICTAL alone. Limited clinical data suggest a higher incidence of headache, dizziness, nausea, and somnolence with coadministration of lamotrigine and oxcarbazepine compared with lamotrigine alone or oxcarbazepine alone.

Phenobarbital, Primidone: The addition of phenobarbital or primidone decreases lamotrigine steady-state concentrations by approximately 40%.

Phenytoin: Lamotrigine has no appreciable effect on steady-state phenytoin plasma concentrations in patients with epilepsy. The addition of phenytoin decreases lamotrigine steady-state concentrations by approximately 40%.

Pregabalin: Steady-state trough plasma concentrations of lamotrigine were not affected by concomitant pregabalin (200 mg 3 times daily) administration. There are no pharmacokinetic interactions between lamotrigine and pregabalin.

Rifampin: In 10 male volunteers, rifampin (600 mg/day for 5 days) significantly increased the apparent clearance of a single 25-mg dose of lamotrigine by approximately 2-fold (AUC decreased by approximately 40%).

Topiramate: Topiramate resulted in no change in plasma concentrations of lamotrigine. Administration of lamotrigine resulted in a 15% increase in topiramate concentrations.

Valproate: When lamotrigine was administered to healthy volunteers (n = 18) receiving valproate, the trough steady-state valproate plasma concentrations decreased by an average of 25% over a 3-week period, and then stabilized. However, adding lamotrigine to the existing therapy did not cause a change in valproate plasma concentrations in either adult or pediatric patients in controlled clinical trials.

The addition of valproate increased lamotrigine steady-state concentrations in normal volunteers by slightly more than 2-fold. In one study, maximal inhibition of lamotrigine clearance was reached at valproate doses between 250 and 500 mg/day and did not increase as the valproate dose was further increased.

Zonisamide: In a study of 18 patients with epilepsy, coadministration of zonisamide (200 to 400 mg/day) with lamotrigine (150 to 500 mg/day for 35 days) had no significant effect on the pharmacokinetics of lamotrigine.

Known Inducers or Inhibitors of Glucuronidation: Drugs other than those listed above have not been systematically evaluated in combination with lamotrigine. Since lamotrigine is metabolized predominately by glucuronic acid conjugation, drugs that are known to induce or inhibit glucuronidation may affect the apparent clearance of lamotrigine and doses of lamotrigine may require adjustment based on clinical response.

Other: Results of in vitro experiments suggest that clearance of lamotrigine is unlikely to be reduced by concomitant administration of amitriptyline, clonazepam, clozapine, fluoxetine, haloperidol, lorazepam, phenelzine, risperidone, sertraline, or trazodone.

Results of in vitro experiments suggest that lamotrigine does not reduce the clearance of drugs eliminated predominantly by CYP2D6.

Special Populations: Patients With Renal Impairment: Twelve volunteers with chronic renal failure (mean creatinine clearance: 13 mL/min, range: 6 to 23) and another 6 individuals undergoing hemodialysis were each given a single 100-mg dose of lamotrigine. The mean plasma half-lives determined in the study were 42.9 hours (chronic renal failure), 13.0 hours (during hemodialysis), and 57.4 hours (between hemodialysis) compared with 26.2 hours in healthy volunteers. On average, approximately 20% (range: 5.6 to 35.1) of the amount of lamotrigine present in the body was eliminated by hemodialysis during a 4-hour session [see Dosage and Administration (2.1)].

Hepatic Disease: The pharmacokinetics of lamotrigine following a single 100-mg dose of lamotrigine were evaluated in 24 subjects with mild, moderate, and severe hepatic impairment (Child-Pugh Classification system) and compared with 12 subjects without hepatic impairment. The patients with severe hepatic impairment were without ascites (n = 2) or with ascites (n = 5). The mean apparent clearances of lamotrigine in patients with mild (n = 12), moderate (n = 5), severe without ascites (n = 2), and severe with ascites (n = 5) liver impairment were 0.30 ± 0.09, 0.24 ± 0.1, 0.21 ± 0.04, and 0.15 ± 0.09 mL/min/kg, respectively, as compared with 0.37 ± 0.1 mL/min/kg in the healthy controls. Mean half-lives of lamotrigine in patients with mild, moderate, severe without ascites, and severe with ascites hepatic impairment were 46 ± 20, 72 ± 44, 67 ± 11, and 100 ± 48 hours, respectively, as compared with 33 ± 7 hours in healthy controls [see Dosage and Administration (2.1)].

Age: Pediatric Patients: The pharmacokinetics of lamotrigine following a single 2-mg/kg dose were evaluated in 2 studies of pediatric patients (n = 29 for patients 10 months to 5.9 years of age and n = 26 for patients 5 to 11 years of age). Forty-three patients received concomitant therapy with other AEDs and 12 patients received lamotrigine as monotherapy. Lamotrigine pharmacokinetic parameters for pediatric patients are summarized in Table 16.

Population pharmacokinetic analyses involving patients 2 to 18 years of age demonstrated that lamotrigine clearance was influenced predominantly by total body weight and concurrent AED therapy. The oral clearance of lamotrigine was higher, on a body weight basis, in pediatric patients than in adults. Weight-normalized lamotrigine clearance was higher in those subjects weighing less than 30 kg, compared with those weighing greater than 30 kg. Accordingly, patients weighing less than 30 kg may need an increase of as much as 50% in maintenance doses, based on clinical response, as compared with subjects weighing more than 30 kg being administered the same AEDs [see Dosage and Administration (2.2)]. These analyses also revealed that, after accounting for body weight, lamotrigine clearance was not significantly influenced by age. Thus, the same weight-adjusted doses should be administered to children irrespective of differences in age. Concomitant AEDs which influence lamotrigine clearance in adults were found to have similar effects in children.

Table 16. Mean Pharmacokinetic Parameters in Pediatric Patients With Epilepsy
Pediatric Study Population | Number of Subjects | Tmax; (hr) | t½; (hr) | Cl/F; (mL/min/kg)
Ages 10 months-5.3 years
Patients taking carbamazepine, phenytoin, phenobarbital, or primidonea | 10 | 3.0; (1.0-5.9) | 7.7; (5.7-11.4) | 3.62; (2.44-5.28)
Patients taking AEDs with no known effect on the apparent clearance of lamotrigine | 7 | 5.2; (2.9-6.1) | 19.0; (12.9-27.1) | 1.2; (0.75-2.42)
Patients taking valproate only | 8 | 2.9; (1.0-6.0) | 44.9; (29.5-52.5) | 0.47; (0.23-0.77)
Ages 5-11 years
Patients taking carbamazepine, phenytoin, phenobarbital, or primidonea | 7 | 1.6; (1.0-3.0) | 7.0; (3.8-9.8) | 2.54; (1.35-5.58)
Patients taking carbamazepine, phenytoin, phenobarbital, or primidonea plus valproate | 8 | 3.3; (1.0-6.4) | 19.1; (7.0-31.2) | 0.89; (0.39-1.93)
Patients taking valproate onlyb | 3 | 4.5; (3.0-6.0) | 65.8; (50.7-73.7) | 0.24; (0.21-0.26)
Ages 13-18 years
Patients taking carbamazepine, phenytoin, phenobarbital, or primidonea | 11 | c | c | 1.3
Patients taking carbamazepine, phenytoin, phenobarbital, or primidonea plus valproate | 8 | c | c | 0.5
Patients taking valproate only | 4 | c | c | 0.3

aCarbamazepine, phenobarbital, phenytoin, and primidone have been shown to increase the apparent clearance of lamotrigine. Estrogen-containing oral contraceptives and rifampin have also been shown to increase the apparent clearance of lamotrigine [see Drug Interactions (7)].

bTwo subjects were included in the calculation for mean Tmax.

cParameter not estimated.

Elderly: The pharmacokinetics of lamotrigine following a single 150-mg dose of LAMICTAL were evaluated in 12 elderly volunteers between the ages of 65 and 76 years (mean creatinine clearance = 61 mL/min, range: 33 to 108 mL/min). The mean half-life of lamotrigine in these subjects was 31.2 hours (range: 24.5 to 43.4 hours), and the mean clearance was 0.40 mL/min/kg (range: 0.26 to 0.48 mL/min/kg).

Gender: The clearance of lamotrigine is not affected by gender. However, during dose escalation of LAMICTAL in one clinical trial in patients with epilepsy on a stable dose of valproate (n = 77), mean trough lamotrigine concentrations, unadjusted for weight, were 24% to 45% higher (0.3 to 1.7 mcg/mL) in females than in males.

Race: The apparent oral clearance of lamotrigine was 25% lower in non-Caucasians than Caucasians.

13 NONCLINICAL TOXICOLOGY

13.1 Carcinogenesis, Mutagenesis, Impairment of Fertility

No evidence of carcinogenicity was seen in 1 mouse study or 2 rat studies following oral administration of lamotrigine for up to 2 years at maximum tolerated doses (30 mg/kg/day for mice and 10 to 15 mg/kg/day for rats, doses that are equivalent to 90 mg/m^2 and 60 to 90 mg/m^2, respectively). Steady-state plasma concentrations ranged from 1 to 4 mcg/mL in the mouse study and 1 to 10 mcg/mL in the rat study. Plasma concentrations associated with the recommended human doses of 300 to 500 mg/day are generally in the range of 2 to 5 mcg/mL, but concentrations as high as 19 mcg/mL have been recorded.

Lamotrigine was not mutagenic in the presence or absence of metabolic activation when tested in 2 gene mutation assays (the Ames test and the in vitro mammalian mouse lymphoma assay). In 2 cytogenetic assays (the in vitro human lymphocyte assay and the in vivo rat bone marrow assay), lamotrigine did not increase the incidence of structural or numerical chromosomal abnormalities.

No evidence of impairment of fertility was detected in rats given oral doses of lamotrigine up to 2.4 times the highest usual human maintenance dose of 8.33 mg/kg/day or 0.4 times the human dose on a mg/m^2 basis. The effect of lamotrigine on human fertility is unknown.

14 CLINICAL STUDIES

14.1 Epilepsy

Monotherapy With LAMICTAL in Adults With Partial Seizures Already Receiving Treatment With Carbamazepine, Phenytoin, Phenobarbital, or Primidone as the Single Antiepileptic Drug: The effectiveness of monotherapy with LAMICTAL was established in a multicenter, double-blind clinical trial enrolling 156 adult outpatients with partial seizures. The patients experienced at least 4 simple partial, complex partial, and/or secondarily generalized seizures during each of 2 consecutive 4-week periods while receiving carbamazepine or phenytoin monotherapy during baseline. LAMICTAL (target dose of 500 mg/day) or valproate (1,000 mg/day) was added to either carbamazepine or phenytoin monotherapy over a 4-week period. Patients were then converted to monotherapy with LAMICTAL or valproate during the next 4 weeks, then continued on monotherapy for an additional 12-week period.

Study endpoints were completion of all weeks of study treatment or meeting an escape criterion. Criteria for escape relative to baseline were: (1) doubling of average monthly seizure count, (2) doubling of highest consecutive 2-day seizure frequency, (3) emergence of a new seizure type (defined as a seizure that did not occur during the 8-week baseline) that is more severe than seizure types that occur during study treatment, or (4) clinically significant prolongation of generalized tonic-clonic seizures. The primary efficacy variable was the proportion of patients in each treatment group who met escape criteria.

The percentages of patients who met escape criteria were 42% (32/76) in the group receiving LAMICTAL and 69% (55/80) in the valproate group. The difference in the percentage of patients meeting escape criteria was statistically significant (P = 0.0012) in favor of LAMICTAL. No differences in efficacy based on age, sex, or race were detected.

Patients in the control group were intentionally treated with a relatively low dose of valproate; as such, the sole objective of this study was to demonstrate the effectiveness and safety of monotherapy with LAMICTAL, and cannot be interpreted to imply the superiority of LAMICTAL to an adequate dose of valproate.

Adjunctive Therapy With LAMICTAL in Adults With Partial Seizures: The effectiveness of LAMICTAL as adjunctive therapy (added to other AEDs) was established in 3 multicenter, placebo-controlled, double-blind clinical trials in 355 adults with refractory partial seizures. The patients had a history of at least 4 partial seizures per month in spite of receiving one or more AEDs at therapeutic concentrations and, in 2 of the studies, were observed on their established AED regimen during baselines that varied between 8 to 12 weeks. In the third, patients were not observed in a prospective baseline. In patients continuing to have at least 4 seizures per month during the baseline, LAMICTAL or placebo was then added to the existing therapy. In all 3 studies, change from baseline in seizure frequency was the primary measure of effectiveness. The results given below are for all partial seizures in the intent-to-treat population (all patients who received at least one dose of treatment) in each study, unless otherwise indicated. The median seizure frequency at baseline was 3 per week while the mean at baseline was 6.6 per week for all patients enrolled in efficacy studies.

One study (n = 216) was a double-blind, placebo-controlled, parallel trial consisting of a 24-week treatment period. Patients could not be on more than 2 other anticonvulsants and valproate was not allowed. Patients were randomized to receive placebo, a target dose of 300 mg/day of LAMICTAL, or a target dose of 500 mg/day of LAMICTAL. The median reductions in the frequency of all partial seizures relative to baseline were 8% in patients receiving placebo, 20% in patients receiving 300 mg/day of LAMICTAL, and 36% in patients receiving 500 mg/day of LAMICTAL. The seizure frequency reduction was statistically significant in the 500-mg/day group compared with the placebo group, but not in the 300-mg/day group.

A second study (n = 98) was a double-blind, placebo-controlled, randomized, crossover trial consisting of two 14-week treatment periods (the last 2 weeks of which consisted of dose tapering) separated by a 4-week washout period. Patients could not be on more than 2 other anticonvulsants and valproate was not allowed. The target dose of LAMICTAL was 400 mg/day. When the first 12 weeks of the treatment periods were analyzed, the median change in seizure frequency was a 25% reduction on LAMICTAL compared with placebo (P<0.001).

The third study (n = 41) was a double-blind, placebo-controlled, crossover trial consisting of two 12-week treatment periods separated by a 4-week washout period. Patients could not be on more than 2 other anticonvulsants. Thirteen patients were on concomitant valproate; these patients received 150 mg/day of LAMICTAL. The 28 other patients had a target dose of 300 mg/day of LAMICTAL. The median change in seizure frequency was a 26% reduction on LAMICTAL compared with placebo (P<0.01).

No differences in efficacy based on age, sex, or race, as measured by change in seizure frequency, were detected.

Adjunctive Therapy With LAMICTAL in Pediatric Patients With Partial Seizures: The effectiveness of LAMICTAL as adjunctive therapy in pediatric patients with partial seizures was established in a multicenter, double-blind, placebo-controlled trial in 199 patients 2 to 16 years of age (n = 98 on LAMICTAL, n = 101 on placebo). Following an 8-week baseline phase, patients were randomized to 18 weeks of treatment with LAMICTAL or placebo added to their current AED regimen of up to 2 drugs. Patients were dosed based on body weight and valproate use. Target doses were designed to approximate 5 mg/kg/day for patients taking valproate (maximum dose: 250 mg/day) and 15 mg/kg/day for the patients not taking valproate (maximum dose: 750 mg/day). The primary efficacy endpoint was percentage change from baseline in all partial seizures. For the intent-to-treat population, the median reduction of all partial seizures was 36% in patients treated with LAMICTAL and 7% on placebo, a difference that was statistically significant (P<0.01).

Adjunctive Therapy With LAMICTAL in Pediatric and Adult Patients With Lennox-Gastaut Syndrome: The effectiveness of LAMICTAL as adjunctive therapy in patients with Lennox-Gastaut syndrome was established in a multicenter, double-blind, placebo-controlled trial in 169 patients 3 to 25 years of age (n = 79 on LAMICTAL, n = 90 on placebo). Following a 4-week single-blind, placebo phase, patients were randomized to 16 weeks of treatment with LAMICTAL or placebo added to their current AED regimen of up to 3 drugs. Patients were dosed on a fixed-dose regimen based on body weight and valproate use. Target doses were designed to approximate 5 mg/kg/day for patients taking valproate (maximum dose: 200 mg/day) and 15 mg/kg/day for patients not taking valproate (maximum dose: 400 mg/day). The primary efficacy endpoint was percentage change from baseline in major motor seizures (atonic, tonic, major myoclonic, and tonic-clonic seizures). For the intent-to-treat population, the median reduction of major motor seizures was 32% in patients treated with LAMICTAL and 9% on placebo, a difference that was statistically significant (P<0.05). Drop attacks were significantly reduced by LAMICTAL (34%) compared with placebo (9%), as were tonic-clonic seizures (36% reduction versus 10% increase for LAMICTAL and placebo, respectively).

Adjunctive Therapy With LAMICTAL in Pediatric and Adult Patients With Primary Generalized Tonic-Clonic Seizures: The effectiveness of LAMICTAL as adjunctive therapy in patients with primary generalized tonic-clonic seizures was established in a multicenter, double-blind, placebo-controlled trial in 117 pediatric and adult patients ≥2 years (n = 58 on LAMICTAL, n = 59 on placebo). Patients with at least 3 primary generalized tonic-clonic seizures during an 8-week baseline phase were randomized to 19 to 24 weeks of treatment with LAMICTAL or placebo added to their current AED regimen of up to 2 drugs. Patients were dosed on a fixed-dose regimen, with target doses ranging from 3 mg/kg/day to 12 mg/kg/day for pediatric patients and from 200 mg/day to 400 mg/day for adult patients based on concomitant AED.

The primary efficacy endpoint was percentage change from baseline in primary generalized tonic-clonic seizures. For the intent-to-treat population, the median percent reduction of primary generalized tonic-clonic seizures was 66% in patients treated with LAMICTAL and 34% on placebo, a difference that was statistically significant (P = 0.006).

14.2 Bipolar Disorder

The effectiveness of LAMICTAL in the maintenance treatment of Bipolar I Disorder was established in 2 multicenter, double-blind, placebo-controlled studies in adult patients who met DSM-IV criteria for Bipolar I Disorder. Study 1 enrolled patients with a current or recent (within 60 days) depressive episode as defined by DSM-IV and Study 2 included patients with a current or recent (within 60 days) episode of mania or hypomania as defined by DSM-IV. Both studies included a cohort of patients (30% of 404 patients in Study 1 and 28% of 171 patients in Study 2) with rapid cycling Bipolar Disorder (4 to 6 episodes per year).

In both studies, patients were titrated to a target dose of 200 mg of LAMICTAL, as add-on therapy or as monotherapy, with gradual withdrawal of any psychotropic medications during an 8- to 16-week open-label period. Overall 81% of 1,305 patients participating in the open-label period were receiving 1 or more other psychotropic medications, including benzodiazepines, selective serotonin reuptake inhibitors (SSRIs), atypical antipsychotics (including olanzapine), valproate, or lithium, during titration of LAMICTAL. Patients with a CGI-severity score of 3 or less maintained for at least 4 continuous weeks, including at least the final week on monotherapy with LAMICTAL, were randomized to a placebo-controlled, double-blind treatment period for up to 18 months. The primary endpoint was TIME (time to intervention for a mood episode or one that was emerging, time to discontinuation for either an adverse event that was judged to be related to Bipolar Disorder, or for lack of efficacy). The mood episode could be depression, mania, hypomania, or a mixed episode.

In Study 1, patients received double-blind monotherapy with LAMICTAL 50 mg/day (n = 50), LAMICTAL 200 mg/day (n = 124), LAMICTAL 400 mg/day (n = 47), or placebo (n = 121). LAMICTAL (200- and 400-mg/day treatment groups combined) was superior to placebo in delaying the time to occurrence of a mood episode. Separate analyses of the 200- and 400-mg/day dose groups revealed no added benefit from the higher dose.

In Study 2, patients received double-blind monotherapy with LAMICTAL (100 to 400 mg/day, n = 59), or placebo (n = 70). LAMICTAL was superior to placebo in delaying time to occurrence of a mood episode. The mean dose of LAMICTAL was about 211 mg/day.

Although these studies were not designed to separately evaluate time to the occurrence of depression or mania, a combined analysis for the 2 studies revealed a statistically significant benefit for LAMICTAL over placebo in delaying the time to occurrence of both depression and mania, although the finding was more robust for depression.

16 HOW SUPPLIED/STORAGE AND HANDLING

LAMICTAL (lamotrigine) Tablets

25 mg, white, scored, shield-shaped tablets debossed with “LAMICTAL” and “25”,

Bottles of 10 | NDC 54868-4673-0
Bottles of 30 | NDC 54868-4673-1

Store at 25°C (77°F); excursions permitted to 15-30°C (59-86°F) [see USP Controlled Room Temperature] in a dry place.

100 mg, peach, scored, shield-shaped tablets debossed with “LAMICTAL” and “100”,

Bottles of 20 | NDC 54868-4675-1
Bottles of 30 | NDC 54868-4675-2
Bottles of 60 | NDC 54868-4675-0
Bottles of 100 | NDC 54868-4675-3

200 mg, blue, scored, shield-shaped tablets debossed with “LAMICTAL” and “200”,

Bottles of 30 | NDC 54868-4916-1
Bottles of 60 | NDC 54868-4916-2
Bottles of 90 | NDC 54868-4916-0

Store at 25°C (77°F); excursions permitted to 15-30°C (59-86°F) [see USP Controlled Room Temperature] in a dry place and protect from light.

17 PATIENT COUNSELING INFORMATION

See FDA-approved patient labeling (Medication Guide).

17.1 Rash

Prior to initiation of treatment with LAMICTAL, the patient should be instructed that a rash or other signs or symptoms of hypersensitivity (e.g., fever, lymphadenopathy) may herald a serious medical event and that the patient should report any such occurrence to a physician immediately.

17.2 Multiorgan Hypersensitivity Reactions, Blood Dyscrasias, and Organ Failure

Patients should be instructed that multiorgan hypersensitivity reactions and acute multiorgan failure may occur with LAMICTAL. Isolated organ failure or isolated blood dyscrasias without evidence of multiorgan hypersensitivity may also occur. Patients should contact their physician immediately if they experience any signs or symptoms of these conditions [see Warnings and Precautions (5.2, 5.3)].

17.3 Suicidal Thinking and Behavior

Patients, their caregivers, and families should be counseled that AEDs, including LAMICTAL, may increase the risk of suicidal thoughts and behavior and should be advised of the need to be alert for the emergence or worsening of symptoms of depression, any unusual changes in mood or behavior, or the emergence of suicidal thoughts, behavior, or thoughts about self-harm. Behaviors of concern should be reported immediately to healthcare providers.

17.4 Worsening of Seizures

Patients should be advised to notify their physician if worsening of seizure control occurs.

17.5 Central Nervous System Adverse Effects

Patients should be advised that LAMICTAL may cause dizziness, somnolence, and other symptoms and signs of CNS depression. Accordingly, they should be advised neither to drive a car nor to operate other complex machinery until they have gained sufficient experience on LAMICTAL to gauge whether or not it adversely affects their mental and/or motor performance.

17.6 Pregnancy and Nursing

Patients should be advised to notify their physicians if they become pregnant or intend to become pregnant during therapy. Patients should be advised to notify their physicians if they intend to breastfeed or are breastfeeding an infant.

Patients should also be encouraged to enroll in the NAAED Pregnancy Registry if they become pregnant. This registry is collecting information about the safety of antiepileptic drugs during pregnancy. To enroll, patients can call the toll-free number 1-888-233-2334 [see Use in Specific Populations (8.1)].

Patients who intend to breastfeed should be informed that LAMICTAL is present in breast milk and that they should monitor their child for potential adverse effects of this drug. Benefits and risks of continuing breastfeeding should be discussed with the patient.

17.7 Oral Contraceptive Use

Women should be advised to notify their physician if they plan to start or stop use of oral contraceptives or other female hormonal preparations. Starting estrogen-containing oral contraceptives may significantly decrease lamotrigine plasma levels and stopping estrogen-containing oral contraceptives (including the “pill-free” week) may significantly increase lamotrigine plasma levels [see Warnings and Precautions (5.8), Clinical Pharmacology (12.3)]. Women should also be advised to promptly notify their physician if they experience adverse reactions or changes in menstrual pattern (e.g., break-through bleeding) while receiving LAMICTAL in combination with these medications.

17.8 Discontinuing LAMICTAL

Patients should be advised to notify their physician if they stop taking LAMICTAL for any reason and not to resume LAMICTAL without consulting their physician.

17.9 Aseptic Meningitis

Patients should be advised that LAMICTAL may cause aseptic meningitis. Patients should be advised to notify their physician immediately if they develop signs and symptoms of meningitis such as headache, fever, nausea, vomiting, stiff neck, rash, abnormal sensitivity to light, myalgia, chills, confusion, or drowsiness while taking LAMICTAL.

17.10 Potential Medication Errors

Medication errors involving LAMICTAL have occurred. In particular the names LAMICTAL or lamotrigine can be confused with the names of other commonly used medications. Medication errors may also occur between the different formulations of LAMICTAL. To reduce the potential of medication errors, write and say LAMICTAL clearly. Depictions of the LAMICTAL Tablets, Chewable Dispersible Tablets, and Orally Disintegrating Tablets can be found in the Medication Guide that accompanies the product to highlight the distinctive markings, colors, and shapes that serve to identify the different presentations of the drug and thus may help reduce the risk of medication errors. To avoid a medication error of using the wrong drug or formulation, patients should be strongly advised to visually inspect their tablets to verify that they are LAMICTAL, as well as the correct formulation of LAMICTAL, each time they fill their prescription [see Dosage Forms and Strengths (3.1, 3.2, 3.3), How Supplied/Storage and Handling (16)].

LAMICTAL is a registered trademark of GlaxoSmithKline.

Microcaps and AdvaTab are registered trademarks of Eurand, Inc.

GlaxoSmithKline

Research Triangle Park, NC 27709

LAMICTAL Tablets and Chewable Dispersible Tablets are manufactured by

DSM Pharmaceuticals, Inc., Greenville, NC 27834 or

GlaxoSmithKline, Research Triangle Park, NC 27709

LAMICTAL Orally Disintegrating Tablets are manufactured by

Eurand, Inc., Vandalia, OH 45377

©2011, GlaxoSmithKline. All rights reserved.

November 2011

LMT:7PI

Relabeling and Repackaging by:
Physicians Total Care, Inc.
Tulsa, Oklahoma 74146

MEDICATION GUIDE

LAMICTAL® (la-MIK-tal)

(lamotrigine)

Tablets and Chewable Dispersible Tablets

LAMICTAL® ODT™

(lamotrigine)

Orally Disintegrating Tablets

Read this Medication Guide before you start taking LAMICTAL and each time you get a refill. There may be new information. This information does not take the place of talking with your healthcare provider about your medical condition or treatment. If you have questions about LAMICTAL, ask your healthcare provider or pharmacist.

What is the most important information I should know about LAMICTAL?

1. LAMICTAL may cause a serious skin rash that may cause you to be hospitalized or even cause death.

There is no way to tell if a mild rash will become more serious. A serious skin rash can happen at any time during your treatment with LAMICTAL, but is more likely to happen within the first 2 to 8 weeks of treatment. Children between 2 to 16 years of age have a higher chance of getting this serious skin rash while taking LAMICTAL.

The risk of getting a serious skin rash is higher if you:

- take LAMICTAL while taking valproate [DEPAKENE® (valproic acid) or DEPAKOTE® (divalproex sodium)]
- take a higher starting dose of LAMICTAL than your healthcare provider prescribed
- increase your dose of LAMICTAL faster than prescribed.

Call your healthcare provider right away if you have any of the following:

- a skin rash
- blistering or peeling of your skin
- hives
- painful sores in your mouth or around your eyes

These symptoms may be the first signs of a serious skin reaction. A healthcare provider should examine you to decide if you should continue taking LAMICTAL.

2. Other serious reactions, including serious blood problems or liver problems. LAMICTAL can also cause other types of allergic reactions or serious problems that may affect organs and other parts of your body like your liver or blood cells. You may or may not have a rash with these types of reactions. Call your healthcare provider right away if you have any of these symptoms:

- fever
- frequent infections
- severe muscle pain
- swelling of your face, eyes, lips, or tongue
- swollen lymph glands
- unusual bruising or bleeding
- weakness, fatigue
- yellowing of your skin or the white part of your eyes

3. Like other antiepileptic drugs, LAMICTAL may cause suicidal thoughts or actions in a very small number of people, about 1 in 500.

Call a healthcare provider right away if you have any of these symptoms, especially if they are new, worse, or worry you:

- thoughts about suicide or dying
- attempt to commit suicide
- new or worse depression
- new or worse anxiety
- feeling agitated or restless
- panic attacks
- trouble sleeping (insomnia)
- new or worse irritability
- acting aggressive, being angry, or violent
- acting on dangerous impulses
- an extreme increase in activity and talking (mania)
- other unusual changes in behavior or mood

Do not stop LAMICTAL without first talking to a healthcare provider.

- Stopping LAMICTAL suddenly can cause serious problems.
- Suicidal thoughts or actions can be caused by things other than medicines. If you have suicidal thoughts or actions, your healthcare provider may check for other causes.

How can I watch for early symptoms of suicidal thoughts and actions?

- Pay attention to any changes, especially sudden changes, in mood, behaviors, thoughts, or feelings.
- Keep all follow-up visits with your healthcare provider as scheduled.
- Call your healthcare provider between visits as needed, especially if you are worried about symptoms.

4. LAMICTAL may rarely cause aseptic meningitis, a serious inflammation of the protective membrane that covers the brain and spinal cord.

Call your healthcare provider right away if you have any of the following symptoms:

- headache
- fever
- nausea
- vomiting
- stiff neck
- rash
- unusual sensitivity to light
- muscle pains
- chills
- confusion
- drowsiness

Meningitis has many causes other than LAMICTAL, which your doctor would check for if you developed meningitis while taking LAMICTAL.

LAMICTAL can have other serious side effects. For more information ask your healthcare provider or pharmacist. Tell your healthcare provider if you have any side effect that bothers you. Be sure to read the section below entitled “What are the possible side effects of LAMICTAL?”

5. Patients prescribed LAMICTAL have sometimes been given the wrong medicine because many medicines have names similar to LAMICTAL, so always check that you receive LAMICTAL.

Taking the wrong medication can cause serious health problems. When your healthcare provider gives you a prescription for LAMICTAL:

- Make sure you can read it clearly.
- Talk to your pharmacist to check that you are given the correct medicine.
- Each time you fill your prescription, check the tablets you receive against the pictures of the tablets below.
  These pictures show the distinct wording, colors, and shapes of the tablets that help to identify the right strength of LAMICTAL Tablets, Chewable Dispersible Tablets, and Orally Disintegrating Tablets. Immediately call your pharmacist if you receive a LAMICTAL tablet that does not look like one of the tablets shown below, as you may have received the wrong medication.

LAMICTAL (lamotrigine) Tablets

25 mg, white

Imprinted with

LAMICTAL 25

100 mg, peach

Imprinted with

LAMICTAL 100

150 mg, cream

Imprinted with

LAMICTAL 150

200 mg, blue

Imprinted with

LAMICTAL 200

LAMICTAL (lamotrigine) Chewable Dispersible Tablets

2 mg, white

Imprinted with

LTG 2

5 mg, white

Imprinted with

GX CL2

25 mg, white

Imprinted with

GX CL5

LAMICTAL ODT (lamotrigine) Orally Disintegrating Tablets

25 mg, white to off-white

Imprinted with LMT on one side

25 on the other

50 mg, white to off-white

Imprinted with

LMT on one side

50 on the other

100 mg, white to off-white

Imprinted with

LAMICTAL on one side

100 on the other

200 mg, white to off-white

Imprinted with

LAMICTAL on one side

200 on the other

What is LAMICTAL?

LAMICTAL is a prescription medicine used:

1. together with other medicines to treat certain types of seizures (partial seizures, primary generalized tonic-clonic seizures, generalized seizures of Lennox-Gastaut syndrome) in people 2 years or older.
2. alone when changing from other medicines used to treat partial seizures in people 16 years or older.
3. for the long-term treatment of Bipolar I Disorder to lengthen the time between mood episodes in people 18 years or older who have been treated for mood episodes with other medicine.

It is not known if LAMICTAL is safe or effective in children or teenagers under the age of 18 with mood disorders such as bipolar disorder or depression.

It is not known if LAMICTAL is safe or effective when used alone as the first treatment of seizures in adults.

Who should not take LAMICTAL?

You should not take LAMICTAL if you have had an allergic reaction to lamotrigine or to any of the inactive ingredients in LAMICTAL. See the end of this leaflet for a complete list of ingredients in LAMICTAL.

What should I tell my healthcare provider before taking LAMICTAL?

Before taking LAMICTAL, tell your healthcare provider about all of your medical conditions, including if you:

- have had a rash or allergic reaction to another antiseizure medicine.
- have or have had depression, mood problems or suicidal thoughts or behavior.
- have had aseptic meningitis after taking LAMICTAL or LAMICTAL XR (lamotrigine).
- are taking oral contraceptives (birth control pills) or other female hormonal medicines. Do not start or stop taking birth control pills or other female hormonal medicine until you have talked with your healthcare provider. Tell your healthcare provider if you have any changes in your menstrual pattern such as breakthrough bleeding. Stopping these medicines may cause side effects (such as dizziness, lack of coordination, or double vision). Starting these medicines may lessen how well LAMICTAL works.
- are pregnant or plan to become pregnant. It is not known if LAMICTAL will harm your unborn baby. If you become pregnant while taking LAMICTAL, talk to your healthcare provider about registering with the North American Antiepileptic Drug Pregnancy Registry. You can enroll in this registry by calling 1-888-233-2334. The purpose of this registry is to collect information about the safety of antiepileptic drugs during pregnancy.
- are breastfeeding. LAMICTAL passes into breast milk and may cause side effects in a breastfed baby. If you breastfeed while taking LAMICTAL, watch your baby closely for trouble breathing, episodes of temporarily stopping breathing, sleepiness, or poor sucking. Call your baby’s healthcare provider right away if you see any of these problems. Talk to your healthcare provider about the best way to feed your baby if you take LAMICTAL.

Tell your healthcare provider about all the medicines you take or if you are planning to take a new medicine, including prescription and non-prescription medicines, vitamins, and herbal supplements. If you use LAMICTAL with certain other medicines, they can affect each other, causing side effects.

How should I take LAMICTAL?

- Take LAMICTAL exactly as prescribed.
- Your healthcare provider may change your dose. Do not change your dose without talking to your healthcare provider.
- Do not stop taking LAMICTAL without talking to your healthcare provider. Stopping LAMICTAL suddenly may cause serious problems. For example, if you have epilepsy and you stop taking LAMICTAL suddenly, you may get seizures that do not stop. Talk with your healthcare provider about how to stop LAMICTAL slowly.
- If you miss a dose of LAMICTAL, take it as soon as you remember. If it is almost time for your next dose, just skip the missed dose. Take the next dose at your regular time. Do not take two doses at the same time.
- You may not feel the full effect of LAMICTAL for several weeks.
- If you have epilepsy, tell your healthcare provider if your seizures get worse or if you have any new types of seizures.
- Swallow LAMICTAL tablets whole.
- If you have trouble swallowing LAMICTAL tablets, tell your healthcare provider because there may be another form of LAMICTAL you can take.
- LAMICTAL ODT should be placed on the tongue and moved around the mouth. The tablet will rapidly disintegrate, can be swallowed with or without water, and can be taken with or without food.
- LAMICTAL Chewable Dispersible tablets may be swallowed whole, chewed, or mixed in water or diluted fruit juice. If the tablets are chewed, drink a small amount of water or diluted fruit juice to help in swallowing. To break up LAMICTAL Chewable Dispersible tablets, add the tablets to a small amount of liquid (1 teaspoon, or enough to cover the medicine) in a glass or spoon. Wait at least 1 minute or until the tablets are completely broken up, mix the solution together and take the whole amount right away.
- If you receive LAMICTAL in a blisterpack, examine the blisterpack before use. Do not use if blisters are torn, broken, or missing.

What should I avoid while taking LAMICTAL?

Do not drive a car or operate complex, hazardous machinery until you know how LAMICTAL affects you.

What are possible side effects of LAMICTAL?

- See “What is the most important information I should know about LAMICTAL?”

Common side effects of LAMICTAL include:

- dizziness

- tremor

- headache

- rash

- blurred or double vision

- fever

- lack of coordination

- abdominal pain

- sleepiness

- back pain

- nausea, vomiting

- tiredness

- insomnia

- dry mouth

Tell your healthcare provider about any side effect that bothers you or that does not go away.

These are not all the possible side effects of LAMICTAL. For more information, ask your healthcare provider or pharmacist.

Call your doctor for medical advice about side effects. You may report side effects to FDA at 1-800-FDA-1088.

How should I store LAMICTAL?

- Store LAMICTAL at room temperature between 68oF to 77oF (20oC to 25oC).
- Keep LAMICTAL and all medicines out of the reach of children.

General information about LAMICTAL

Medicines are sometimes prescribed for purposes other than those listed in a Medication Guide. Do not use LAMICTAL for a condition for which it was not prescribed. Do not give LAMICTAL to other people, even if they have the same symptoms you have. It may harm them.

This Medication Guide summarizes the most important information about LAMICTAL. If you would like more information, talk with your healthcare provider. You can ask your healthcare provider or pharmacist for information about LAMICTAL that is written for healthcare professionals.

For more information, go to www.lamictal.com or call 1-888-825-5249.

What are the ingredients in LAMICTAL?

LAMICTAL Tablets

Active ingredient: lamotrigine.

Inactive ingredients: lactose; magnesium stearate, microcrystalline cellulose, povidone, sodium starch glycolate, FD&C Yellow No. 6 Lake (100 mg tablet only), ferric oxide, yellow (150 mg tablet only), and FD&C Blue No. 2 Lake (200 mg tablet only).

LAMICTAL Chewable Dispersible Tablets

Active ingredient: lamotrigine.

Inactive ingredients: blackcurrant flavor, calcium carbonate, low-substituted hydroxypropylcellulose, magnesium aluminum silicate, magnesium stearate, povidone, saccharin sodium, and sodium starch glycolate.

LAMICTAL ODT Orally Disintegrating Tablets

Active ingredient: lamotrigine

Inactive ingredients: artificial cherry flavor, crospovidone, ethylcellulose, magnesium stearate, mannitol, polyethylene, and sucralose.

This Medication Guide has been approved by the U.S. Food and Drug Administration.

LAMICTAL is a registered trademark of GlaxoSmithKline.

DEPAKENE and DEPAKOTE are registered trademarks of Abbott Laboratories.

GlaxoSmithKline

Research Triangle Park, NC 27709

LAMICTAL Tablets and Chewable Dispersible Tablets are manufactured by

DSM Pharmaceuticals, Inc.,

Greenville, NC 27834 or

GlaxoSmithKline

Research Triangle Park, NC 27709

LAMICTAL Orally Disintegrating Tablets are manufactured by

Eurand, Inc., Vandalia, OH 45377

©2011, GlaxoSmithKline. All rights reserved.

December 2011

LMT:7MG

PACKAGE LABEL

Principal Display Panel

LAMICTAL®

(LAMOTRIGINE)

TABLETS

25 mg

Rx only

CAUTION: Verify Product Dispensed

Dispense the accompanying Medication Guide to each patient.

Each scored tablet contains 25 mg of lamotrigine.

See Prescribing Information for dosage information.

Store at 25oC (77oF); excursions 15-30oC (59-86oF) in a dry place.

Dispense in a tight container as defined in the USP.

PACKAGE LABEL

Principal Display Panel

LAMICTAL®

(LAMOTRIGINE)

TABLETS

100 mg

Rx only

CAUTION: Verify Product Dispensed

Dispense the accompanying Medication Guide to each patient.

Each scored tablet contains 100 mg of lamotrigine.

See Prescribing Information for dosage information.

Store at 25oC (77oF); excursions 15-30oC (59-86oF) in a dry place.

Dispense in a tight, light-resistant container as defined in the USP.

PACKAGE LABEL

Principal Display Panel

LAMICTAL®

(LAMOTRIGINE)

TABLETS

200 mg

Rx only

CAUTION: Verify Product Dispensed

Dispense the accompanying Medication Guide to each patient.

Each scored tablet contains 150 mg of lamotrigine.

See Prescribing Information for dosage information.

Store at 25oC (77oF); excursions 15-30oC (59-86oF) in a dry place.

Dispense in a tight, light-resistant container as defined in the USP.